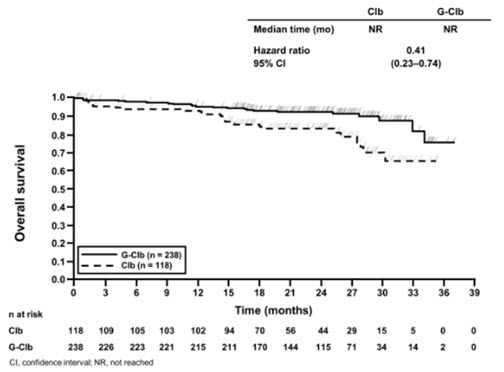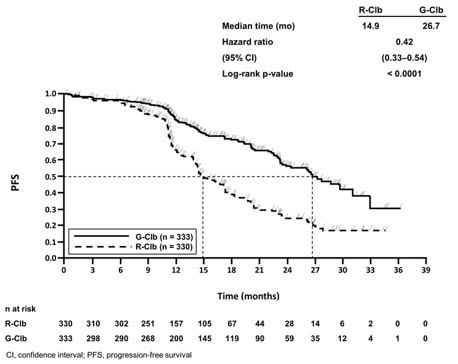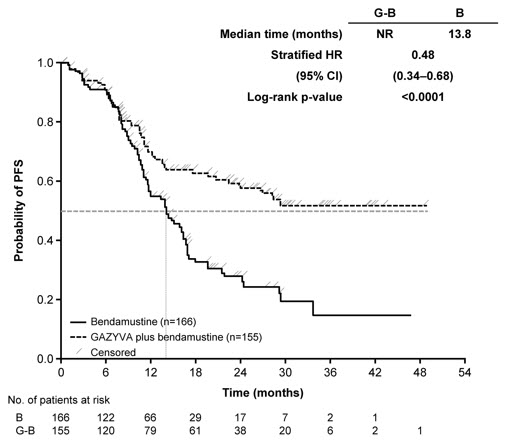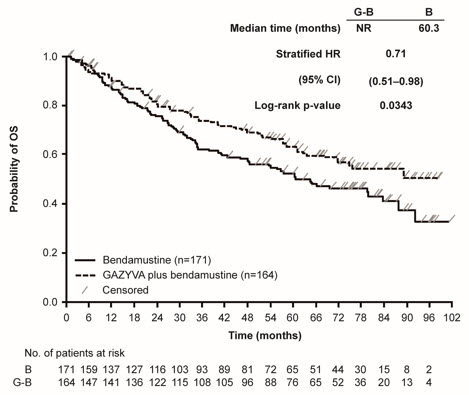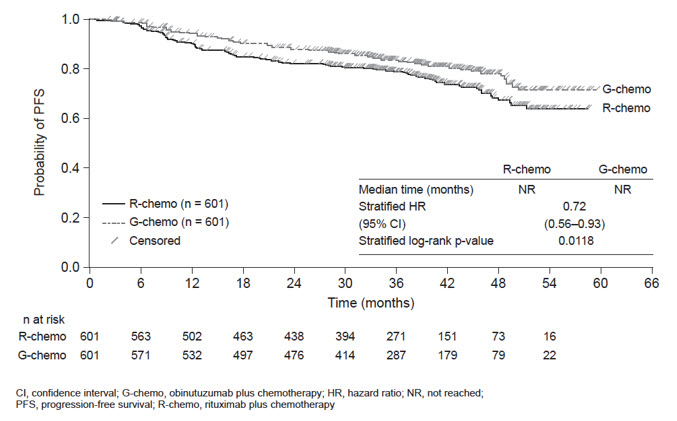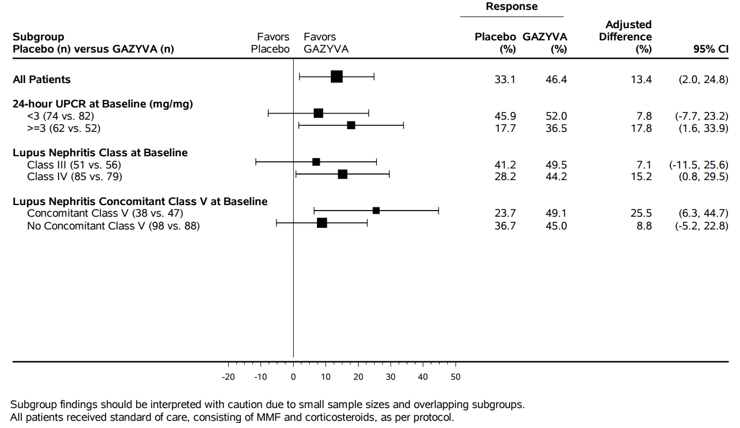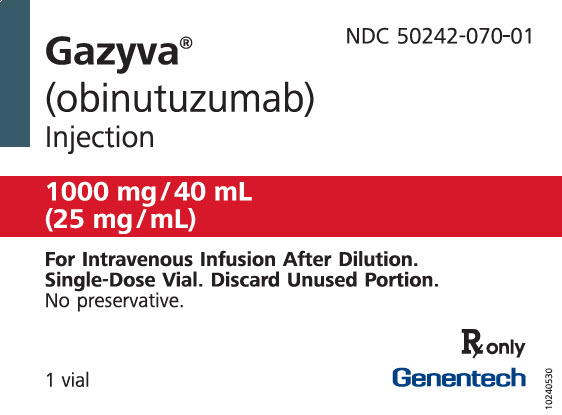 DRUG LABEL: Gazyva
NDC: 50242-070 | Form: INJECTION, SOLUTION, CONCENTRATE
Manufacturer: Genentech, Inc.
Category: prescription | Type: HUMAN PRESCRIPTION DRUG LABEL
Date: 20251219

ACTIVE INGREDIENTS: OBINUTUZUMAB 1000 mg/40 mL
INACTIVE INGREDIENTS: HISTIDINE; HISTIDINE HYDROCHLORIDE MONOHYDRATE; TREHALOSE DIHYDRATE; POLOXAMER 188; WATER

HIGHLIGHTS OF PRESCRIBING INFORMATION

These highlights do not include all the information needed to use GAZYVA safely and effectively. See full prescribing information for GAZYVA.
GAZYVA® (obinutuzumab) injection, for intravenous use
Initial U.S. Approval: 2013

WARNING: HEPATITIS B VIRUS REACTIVATION and PROGRESSIVE MULTIFOCAL LEUKOENCEPHALOPATHY

See full prescribing information for complete boxed warning.

- Hepatitis B Virus (HBV) reactivation, in some cases resulting in fulminant hepatitis, hepatic failure, and death. (5.1)
- Progressive Multifocal Leukoencephalopathy (PML) resulting in death. (5.2)

RECENT MAJOR CHANGES

Indication and Usage, Lupus Nephritis (1.3) | 10/2025
Dosage and Administration (2.4) | 10/2025
Warnings and Precautions (5) | 10/2025

1 INDICATIONS AND USAGE

GAZYVA is a CD20-directed cytolytic antibody indicated:

- in combination with chlorambucil, for the treatment of patients with previously untreated chronic lymphocytic leukemia (CLL). (1.1, 14)
- in combination with bendamustine followed by GAZYVA monotherapy, for the treatment of patients with follicular lymphoma (FL)who relapsed after, or are refractory to, a rituximab-containing regimen. (1.2, 14)
- in combination with chemotherapy followed by GAZYVA monotherapy in patients achieving at least a partial remission, for the treatment of adult patients with previously untreated stage II bulky, III or IV follicular lymphoma. (1.2, 14)
- for the treatment of adult patients with active lupus nephritis (LN) who are receiving standard therapy (1.3, 14)

2 DOSAGE AND ADMINISTRATION

- Premedicate for infusion-related reactions and tumor lysis syndrome. (2.1, 5.3, 5.4)
- Administer only as intravenous infusion. Do not administer as an intravenous push or bolus. (2.1)
- The recommended dosage for chronic lymphocytic leukemia is 100 mg on day 1 and 900 mg on day 2 of Cycle 1, 1,000 mg on day 8 and 15 of Cycle 1, and 1,000 mg on day 1 of Cycles 2–6. (2.2)
- The recommended dosage for follicular lymphoma is 1,000 mg on day 1, 8 and 15 of Cycle 1, 1,000 mg on day 1 of Cycles 2-6 or Cycles 2-8, and then 1,000 mg every 2 months for up to 2 years. (2.3)
- The recommended dosage for active lupus nephritis is 1,000 mg at the initial infusion, on Week 2, 24, 26, and every 6 months thereafter. (2.4)

3 DOSAGE FORMS AND STRENGTHS

Injection: 1,000 mg/40 mL (25 mg/mL) single-dose vial. (3)

4 CONTRAINDICATIONS

GAZYVA is contraindicated in patients with known hypersensitivity reactions (e.g., anaphylaxis) to obinutuzumab or any of the excipients, including serum sickness with prior obinutuzumab use. (4)

5 WARNINGS AND PRECAUTIONS

- Infusion-Related Reactions: Premedicate patients with glucocorticoid, acetaminophen, and anti-histamine. Monitor patients closely during infusions. Interrupt, reduce rate, or discontinue for infusion-related reactions based on severity. (2.1, 5.3)
- Hypersensitivity Reactions Including Serum Sickness: Discontinue GAZYVA permanently. (5.4)
- Tumor Lysis Syndrome: In CLL and FL, premedicate with anti-hyperuricemics and adequate hydration, especially for patients with high tumor burden, high circulating lymphocyte count or renal impairment. Correct electrolyte abnormalities, provide supportive care, and monitor renal function and fluid balance. (5.5)
- Serious, Including Fatal, Infections: Do not administer GAZYVA to patients with an active infection. Patients with a history of recurring or chronic infections may be at increased risk of infection. (5.6)
- Neutropenia: In patients with Grade 3 to 4 neutropenia, monitor laboratory tests until resolution and for infection. Consider dose delays and infection prophylaxis, as appropriate. (5.7)
- Thrombocytopenia: Monitor for decreased platelet counts and bleeding. Transfusion may be necessary. (5.8)
- Disseminated Intravascular Coagulation: Evaluate cause and monitor for bleeding, thrombosis, and need for supportive care. (5.9)
- Immunization: Avoid administration of live virus vaccines during GAZYVA treatment and until B-cell recovery. (5.10)
- Embryo-Fetal Toxicity: Can cause fetal harm. Advise females of reproductive potential of the potential risk to a fetus and use effective contraception. (5.11)

6 ADVERSE REACTIONS

The most common adverse reactions (incidence ≥ 20% and ≥ 2% greater in the GAZYVA treated arm in CLL and NHL, and incidence ≥ 5% in the GAZYVA treated arm in LN) were:

- Previously untreated CLL: infusion-related reactions and neutropenia. (6)
- Relapsed or refractory non-Hodgkin lymphoma (NHL): infusion-related reactions, fatigue, neutropenia, cough, upper respiratory tract infections, and musculoskeletal pain. (6)
- Previously untreated NHL: infusion-related reactions, neutropenia, upper respiratory tract infections, cough, constipation, and diarrhea. (6)
- Lupus Nephritis: upper respiratory tract infection, COVID-19, urinary tract infection, bronchitis, pneumonia, infusion-related reactions, and neutropenia. (6)

To report SUSPECTED ADVERSE REACTIONS, contact Genentech at 1-888-835-2555 or FDA at 1-800-FDA-1088 or www.fda.gov/medwatch.

8 USE IN SPECIFIC POPULATIONS

- Lactation: Advise not to breastfeed. (8.1)

FULL PRESCRIBING INFORMATION

WARNING: HEPATITIS B VIRUS REACTIVATION and PROGRESSIVE MULTIFOCAL LEUKOENCEPHALOPATHY

- Hepatitis B Virus (HBV) reactivation, in some cases resulting in fulminant hepatitis, hepatic failure, and death, can occur in patients receiving CD20-directed cytolytic antibodies, including GAZYVA. Screen all patients for HBV infection before treatment initiation. Monitor HBV-positive patients during and after treatment with GAZYVA. Discontinue GAZYVA and concomitant medications in the event of HBV reactivation [see Warnings and Precautions (5.1)].
- Progressive Multifocal Leukoencephalopathy (PML) including fatal PML, can occur in patients receiving GAZYVA [see Warnings and Precautions (5.2)].

1 INDICATIONS AND USAGE

1.1 Chronic Lymphocytic Leukemia (CLL)

GAZYVA, in combination with chlorambucil, is indicated for the treatment of patients with previously untreated chronic lymphocytic leukemia.

1.2 Follicular Lymphoma (FL)

GAZYVA, in combination with bendamustine followed by GAZYVA monotherapy, is indicated for the treatment of patients with follicular lymphoma who relapsed after, or are refractory to, a rituximab-containing regimen.

GAZYVA, in combination with chemotherapy followed by GAZYVA monotherapy in patients achieving at least a partial remission, is indicated for the treatment of adult patients with previously untreated stage II bulky, III or IV follicular lymphoma.

1.3 Lupus Nephritis (LN)

GAZYVA is indicated for the treatment of adult patients with active lupus nephritis who are receiving standard therapy.

2 DOSAGE AND ADMINISTRATION

2.1 Important Dosing Information

- Premedicate before each infusion [see Dosage and Administration (2.4)].
- Provide prophylactic hydration and anti-hyperuricemics to patients at high risk of tumor lysis syndrome [see Dosage and Administration (2.4) and Warnings and Precautions (5.4)].
- Administer only as an intravenous infusion through a dedicated line [see Dosage and Administration (2.6)].
- Do not administer as an intravenous push or bolus.
- Monitor blood counts at regular intervals.
- GAZYVA should only be administered by a healthcare professional with appropriate medical support to manage severe infusion-related reactions that can be fatal if they occur [see Warnings and Precautions (5.3)].

2.2 Recommended Dosage for Chronic Lymphocytic Leukemia

Each dose of GAZYVA is 1,000 mg administered intravenously with the exception of the first infusions in Cycle 1, which are administered on day 1 (100 mg) and day 2 (900 mg) according to Table 1.

Table 1 Dose of GAZYVA to be Administered During Six 28-Day Treatment Cycles for Patients with CLL
Day of treatment cycle |  | Dose of GAZYVA | Rate of infusion
Cycle 1 (loading doses) | Day 1 | 100 mg | Administer at 25 mg/hr over 4 hours. Do not increase the infusion rate.
Cycle 1 (loading doses) | Day 2 | 900 mg | If no infusion-related reaction (IRR) occurred during the previous infusion, administer at 50 mg/hr. The rate of the infusion can be escalated in increments of 50 mg/hr every 30 minutes to a maximum rate of 400 mg/hr. If an IRR occurred during the previous infusion, administer at 25 mg/hr. The rate of infusion can be escalated in increments of up to 50 mg/hr every 30 minutes to a maximum rate of 400 mg/hr.
Cycle 1 (loading doses) | Day 8 | 1,000 mg | If no IRR occurred during the previous infusion and the final infusion rate was 100 mg/hr or faster, infusions can be started at a rate of 100 mg/hr and increased by 100 mg/hr increments every 30 minutes to a maximum of 400 mg/hr. If an infusion-related reaction occurred during the previous infusion, administer at 50 mg/hr. The rate of infusion can be escalated in increments of 50 mg/hr every 30 minutes to a maximum rate of 400 mg/hr.
Cycle 1 (loading doses) | Day 15 | 1,000 mg | If no IRR occurred during the previous infusion and the final infusion rate was 100 mg/hr or faster, infusions can be started at a rate of 100 mg/hr and increased by 100 mg/hr increments every 30 minutes to a maximum of 400 mg/hr. If an infusion-related reaction occurred during the previous infusion, administer at 50 mg/hr. The rate of infusion can be escalated in increments of 50 mg/hr every 30 minutes to a maximum rate of 400 mg/hr.
Cycles 2–6 | Day 1 | 1,000 mg | If no IRR occurred during the previous infusion and the final infusion rate was 100 mg/hr or faster, infusions can be started at a rate of 100 mg/hr and increased by 100 mg/hr increments every 30 minutes to a maximum of 400 mg/hr. If an infusion-related reaction occurred during the previous infusion, administer at 50 mg/hr. The rate of infusion can be escalated in increments of 50 mg/hr every 30 minutes to a maximum rate of 400 mg/hr.

If a planned dose of GAZYVA is missed, administer the missed dose as soon as possible and adjust dosing schedule to maintain the time interval between doses. If appropriate, patients who do not complete the Day 1 Cycle 1 dose may proceed to the Day 2 Cycle 1 dose.

2.3 Recommended Dosage for Follicular Lymphoma

Each dose of GAZYVA is 1,000 mg administered intravenously according to Table 2.

For patients with relapsed or refractory FL, administer GAZYVA in combination with bendamustine in six 28-day cycles. Patients who achieve stable disease, complete response, or partial response to the initial 6 cycles should continue on GAZYVA 1,000 mg as monotherapy for up to two years.

For patients with previously untreated FL, administer GAZYVA with one of the following chemotherapy regimens:

- Six 28-day cycles in combination with bendamustine
- Six 21-day cycles in combination with CHOP, followed by 2 additional 21-day cycles of GAZYVA alone
- Eight 21-day cycles in combination with CVP

Patients with previously untreated FL who achieve a complete response or partial response to the initial 6 or 8 cycles should continue on GAZYVA 1,000 mg as monotherapy for up to two years.

GAZYVA should be administered at the standard infusion rate in Cycle 1 (see Table 2). In patients with FL who do not experience a Grade 3 or higher IRR during Cycle 1, GAZYVA may be administered as a shorter, approximately 90-minute infusion from Cycle 2 onwards (see Table 3) with continued premedication.

Table 2 Dose and Standard Infusion Rate of GAZYVA to be Administered During 6–8 Treatment Cycles, Followed by GAZYVA Monotherapy for Patients with FL
Day of treatment cycle |  | Dose of GAZYVA | Rate of infusion
Cycle 1 (loading doses) | Day 1 | 1,000 mg | Administer at 50 mg/hr. The rate of the infusion can be escalated in 50 mg/hr increments every 30 minutes to a maximum of 400 mg/hr.
Cycle 1 (loading doses) | Day 8 | 1,000 mg | If no infusion-related reaction or an infusion-related reaction of Grade 1 occurred during the previous infusion and the final infusion rate was 100 mg/hr or faster, infusions can be started at a rate of 100 mg/hr and increased by 100 mg/hr increments every 30 minutes to a maximum of 400 mg/hr. If an infusion-related reaction of Grade 2 or higher occurred during the previous infusion, administer at 50 mg/hr. The rate of infusion can be escalated in increments of 50 mg/hr every 30 minutes to a maximum rate of 400 mg/hr.
Cycle 1 (loading doses) | Day 15 | 1,000 mg | If no infusion-related reaction or an infusion-related reaction of Grade 1 occurred during the previous infusion and the final infusion rate was 100 mg/hr or faster, infusions can be started at a rate of 100 mg/hr and increased by 100 mg/hr increments every 30 minutes to a maximum of 400 mg/hr. If an infusion-related reaction of Grade 2 or higher occurred during the previous infusion, administer at 50 mg/hr. The rate of infusion can be escalated in increments of 50 mg/hr every 30 minutes to a maximum rate of 400 mg/hr.
Cycles 2–6 or 2–8 | Day 1 | 1,000 mg | If no infusion-related reaction or an infusion-related reaction of Grade 1 occurred during the previous infusion and the final infusion rate was 100 mg/hr or faster, infusions can be started at a rate of 100 mg/hr and increased by 100 mg/hr increments every 30 minutes to a maximum of 400 mg/hr. If an infusion-related reaction of Grade 2 or higher occurred during the previous infusion, administer at 50 mg/hr. The rate of infusion can be escalated in increments of 50 mg/hr every 30 minutes to a maximum rate of 400 mg/hr.
Monotherapy | Every two months for up to two years | 1,000 mg | If no infusion-related reaction or an infusion-related reaction of Grade 1 occurred during the previous infusion and the final infusion rate was 100 mg/hr or faster, infusions can be started at a rate of 100 mg/hr and increased by 100 mg/hr increments every 30 minutes to a maximum of 400 mg/hr. If an infusion-related reaction of Grade 2 or higher occurred during the previous infusion, administer at 50 mg/hr. The rate of infusion can be escalated in increments of 50 mg/hr every 30 minutes to a maximum rate of 400 mg/hr.

Table 3 Dose and Infusion Rate of a GAZYVA 90-Minute Infusion for Patients with FL
Day of treatment cycle |  | Dose of GAZYVA | Rate of infusion
Cycle 1 | Days 1, 8, 15 | 1,000 mg | See Table 2
Cycles 2–6 [Consider an approximately 90-minute infusion in patients with FL who do not experience a Grade 3 or higher infusion-related reaction to GAZYVA in Cycle 1 and subsequent cycles.] or 2-8 | Day 1 | 1,000 mg | If no Grade 3 or higher IRR occurred during Cycle 1: 100 mg/hr for 30 minutes, then 900 mg/hr for approximately 60 minutes. If an IRR of Grade 1-2 with ongoing symptoms or a Grade 3 or higher IRR occurred during the previous approximately 90-minute infusion, administer all subsequent GAZYVA infusions at the standard infusion rate (see Table 2).
Monotherapy | Every two months for up to two years | 1,000 mg | If no Grade 3 or higher IRR occurred during Cycle 1: 100 mg/hr for 30 minutes, then 900 mg/hr for approximately 60 minutes. If an IRR of Grade 1-2 with ongoing symptoms or a Grade 3 or higher IRR occurred during the previous approximately 90-minute infusion, administer all subsequent GAZYVA infusions at the standard infusion rate (see Table 2).

If a planned dose of GAZYVA is missed, administer the missed dose as soon as possible. During GAZYVA and chemotherapy treatment, adjust the dosing schedule accordingly to maintain the time interval between chemotherapy cycles. During monotherapy, maintain the original dosing schedule for subsequent doses. Initiate monotherapy approximately two months after the last dose of GAZYVA administered during the induction phase.

2.4 Recommended Dosage for Active Lupus Nephritis

Each recommended dose of GAZYVA is 1,000 mg administered intravenously according to Table 4.

Table 4 Dose and Infusion Rate for Standard Infusion of GAZYVA in Adults with Active Lupus Nephritis
Dose number | Timing of treatment | Dose of GAZYVA | Rate of infusion
1 | Initial infusion | 1,000 mg | Administer at a rate of 50 mg/hr. The rate of infusion can be escalated in 50 mg/hr increments every 30 minutes to a maximum of 400 mg/hr. For management of IRRs that occur during infusion, see Dosage Modifications for Adverse Reactions (2.6).
2 | Week 2 (two weeks after Dose 1) | 1,000 mg | Administer at a rate of 100 mg/hr. The rate of infusion can be escalated at a rate of 100 mg/hr every 30 minutes to a maximum of 400 mg/hr.
3 | Week 24 | 1,000 mg | Administer at a rate of 100 mg/hr. The rate of infusion can be escalated at a rate of 100 mg/hr every 30 minutes to a maximum of 400 mg/hr.
4 | Week 26 (two weeks after Dose 3) | 1,000 mg | Administer at a rate of 100 mg/hr. The rate of infusion can be escalated at a rate of 100 mg/hr every 30 minutes to a maximum of 400 mg/hr.
5 [Dose 5 should be administered six months after Dose 4] and thereafter | Every 6 months | 1,000 mg | Administer at a rate of 100 mg/hr. The rate of infusion can be escalated at a rate of 100 mg/hr every 30 minutes to a maximum of 400 mg/hr.

Patients who do not experience Grade ≥ 3 infusion related reactions during the previous infusion may receive GAZYVA over approximately 90 minutes from Dose 2 onwards (see Table 5), with continued premedication.

Table 5 Dose and Infusion Rate for a 90-Minute Infusion of GAZYVA in Adults with Active Lupus Nephritis
Dose number | Rate of infusion
1 | See Table 4
2 and thereafter (if no Grade 3 or higher IRR during previous infusion) | 100 mg/hr for 30 minutes, then 900 mg/hr for approximately 60 minutes. If an IRR of Grade 1-2 with ongoing symptoms or a Grade 3 or higher IRR occurs during the previous approximately 90-minute infusion, administer GAZYVA at the standard infusion rate (see Table 4).

If a planned dose of GAZYVA is missed, it should be administered as soon as possible – do not wait until the next planned dose. The schedule of administration should be adjusted to maintain the appropriate interval between doses.

2.5 Recommended Premedication and Prophylactic Medications

Infusion-Related Reactions

Premedication to reduce the risk of IRRs is outlined in Table 6 [see Warnings and Precautions (5.3)].

Hypotension may occur during GAZYVA intravenous infusions. Consider withholding antihypertensive treatments for 12 hours prior to and throughout each GAZYVA infusion and for the first hour after administration [see Warnings and Precautions (5.3)].

Table 6 Premedication for GAZYVA Infusion to Reduce Infusion-Related Reactions
Indication/Cycle/Day of Treatment | Patients requiring premedication | Premedication | Administration
CLL Cycle 1 Days 1 and 2 FL Cycle 1 Day 1 | All patients | Intravenous glucocorticoid: 20 mg dexamethasone or 80 mg methylprednisolone [Hydrocortisone is not recommended as it has not been effective in reducing the rate of IRRs.] , [If a glucocorticoid-containing chemotherapy regimen is administered on the same day as GAZYVA, the glucocorticoid can be administered as an oral medication if given at least 1 hour prior to GAZYVA, in which case additional intravenous glucocorticoid as premedication is not required.] | Completed at least 1 hour prior to GAZYVA infusion.
CLL Cycle 1 Days 1 and 2 FL Cycle 1 Day 1 | All patients | 650–1,000 mg acetaminophen | At least 30 minutes before GAZYVA infusion.
CLL Cycle 1 Days 1 and 2 FL Cycle 1 Day 1 | All patients | anti-histamine (e.g., 50 mg diphenhydramine) | At least 30 minutes before GAZYVA infusion.
CLL or FL All subsequent infusions | All patients | 650–1,000 mg acetaminophen | At least 30 minutes before GAZYVA infusion.
CLL or FL All subsequent infusions | Patients with an IRR (Grade 1-2) with the previous infusion | 650–1,000 mg acetaminophen | At least 30 minutes before GAZYVA infusion.
CLL or FL All subsequent infusions | Patients with an IRR (Grade 1-2) with the previous infusion | anti-histamine (e.g., 50 mg diphenhydramine) | At least 30 minutes before GAZYVA infusion.
CLL or FL All subsequent infusions | Patients with a Grade 3 IRR with the previous infusion OR with a lymphocyte count > 25 × 10^9/L prior to next treatment | Intravenous glucocorticoid: 20 mg dexamethasone or 80 mg methylprednisolone | Completed at least 1 hour prior to GAZYVA infusion.
CLL or FL All subsequent infusions | Patients with a Grade 3 IRR with the previous infusion OR with a lymphocyte count > 25 × 10^9/L prior to next treatment | 650–1,000 mg acetaminophen | At least 30 minutes before GAZYVA infusion.
CLL or FL All subsequent infusions | Patients with a Grade 3 IRR with the previous infusion OR with a lymphocyte count > 25 × 10^9/L prior to next treatment | anti-histamine (e.g., 50 mg diphenhydramine) | At least 30 minutes before GAZYVA infusion.
LN | All patients | Intravenous glucocorticoid (80 mg methylprednisolone) | Completed between 30 and 60 minutes prior to GAZYVA infusion Starting from Dose 6, intravenous corticosteroid should only be administered to patients who have experienced an IRR in the prior infusion
LN | All patients | 650–1,000 mg acetaminophen | Completed between 30 and 60 minutes prior to GAZYVA infusion Starting from Dose 6, intravenous corticosteroid should only be administered to patients who have experienced an IRR in the prior infusion
LN | All patients | anti-histamine (e.g., 50 mg diphenhydramine) | Completed between 30 and 60 minutes prior to GAZYVA infusion Starting from Dose 6, intravenous corticosteroid should only be administered to patients who have experienced an IRR in the prior infusion
Premedication applies to both standard and approximately 90-minute infusions.

Tumor Lysis Syndrome Prophylaxis

Patients with high tumor burden, high circulating absolute lymphocyte counts (greater than 25 × 10^9/L) or renal impairment are considered at risk of tumor lysis syndrome and should receive prophylaxis. Premedicate with anti-hyperuricemics (e.g., allopurinol or rasburicase) and ensure adequate hydration prior to start of GAZYVA therapy. Continue prophylaxis prior to each subsequent GAZYVA infusion, as needed [see Warnings and Precautions (5.4)].

Antimicrobial Prophylaxis

Patients with Grade 3 to 4 neutropenia lasting more than one week are strongly recommended to receive antimicrobial prophylaxis until resolution of neutropenia to Grade 1 or 2. Consider antiviral and antifungal prophylaxis for patients with severe and long lasting (> 1 week) neutropenia.

2.6 Dosage Modifications for Adverse Reactions

Infusion-Related Reactions

If a patient experiences an IRR, adjust the infusion as follows [see Warnings and Precautions (5.3)]:

- Grade 4 (life-threatening): Stop infusion immediately and permanently discontinue GAZYVA.
- Grade 3 (severe): Interrupt infusion and manage symptoms.
  - For patients who experience Grade 3 IRRs during standard infusion, upon resolution of symptoms, consider restarting GAZYVA infusion at no more than half the previous rate (the rate being used at the time that the IRR reaction occurred), and if patient does not experience any further IRR symptoms, infusion rate escalation may resume at the increments and intervals as appropriate for the treatment cycle dose. Permanently discontinue treatment if patients experience a Grade 3 or higher IRR at rechallenge.
  - For patients with FL who experience Grade 3 IRRs during the approximately 90-minute infusion, upon resolution of symptoms, the infusion can be restarted at no more than half the previous rate (the rate being used at the time that the IRR occurred) and not greater than 400 mg/hr. Administer subsequent infusions at the standard rate. Permanently discontinue treatment if patients experience a Grade 3 or higher IRR at rechallenge.
  - For patients with CLL only, the Day 1 infusion rate may be increased back up to 25 mg/hr after 1 hour but not increased further.
- Grade 1–2 (mild to moderate): Reduce infusion rate or interrupt infusion and manage symptoms. Upon resolution of symptoms, continue or resume GAZYVA infusion, and if patient does not experience any further IRR symptoms, infusion rate escalation may resume at the increments and intervals as appropriate for the treatment cycle dose.
  - For patients with CLL only, the Day 1 infusion rate may be increased back up to 25 mg/hr after 1 hour but not increased further.
  - For patients with LN, reduce infusion rate to half the rate that was used at the time of the reaction and treat symptoms. Upon resolution of symptoms, the infusion should be kept at the reduced rate for an additional 30 minutes. If no further symptoms of IRR, infusion rate escalation may resume at the increments and intervals as appropriate for the treatment dose.

Other Adverse Reactions

Consider treatment interruption if patients experience an infection, Grade 3 or 4 cytopenia, or Grade 2 or higher non-hematologic toxicity.

2.7 Preparation and Administration

Preparation

Prepare the solution for infusion, using aseptic technique, as follows:

- Inspect visually for any particulate matter and discoloration prior to administration.
- Use a sterile needle and syringe to prepare GAZYVA.
- Dilute into a 0.9% Sodium Chloride Injection, USP PVC or non-PVC polyolefin infusion bag.
  Chronic Lymphocytic Leukemia
  - Preparation of solution for infusion on day 1 (100 mg) and day 2 (900 mg) of Cycle 1:
    - Prepare day 1 (100 mg) and day 2 (900 mg) infusion bags at the same time using one vial (1,000 mg/40 mL) on day 1.
    - Withdraw 40 mL of GAZYVA solution from the vial.
    - Dilute 4 mL (100 mg) of GAZYVA into a 100 mL 0.9% Sodium Chloride Injection, USP infusion bag for immediate administration.
    - Dilute the remaining 36 mL (900 mg) into a 250 mL 0.9% Sodium Chloride Injection, USP infusion bag at the same time for use on day 2 and store in a refrigerator at 2°C to 8°C (36°F to 46°F) for up to 24 hours. After allowing the diluted bag to come to room temperature, use immediately.
    - Clearly label each infusion bag.
  - Preparation of solution for infusion on day 8 and 15 of Cycle 1 and day 1 of Cycles 2–6:
    - Withdraw 40 mL of GAZYVA solution from the vial.
    - Dilute 40 mL (1,000 mg) into a 250 mL 0.9% Sodium Chloride Injection, USP infusion bag.
  Follicular Lymphoma and Active Lupus Nephritis
  - Preparation of solution for infusion:
    - Withdraw 40 mL of GAZYVA solution from the vial.
    - Dilute 40 mL (1,000 mg) into a 250 mL 0.9% Sodium Chloride Injection, USP infusion bag.
- Mix diluted solution by gentle inversion. Do not shake or freeze.
- For microbiological stability, immediately use diluted GAZYVA infusion solution. If not used immediately, store in a refrigerator at 2°C to 8°C (36°F to 46°F) for up to 24 hours prior to use.

The product can be administered at a final concentration of 0.4 mg/mL to 4 mg/mL.

Storage

Use the diluted solution immediately. If not used immediately, store for up to 24 hours at 2°C to 8°C. Discard after 24 hours.

Administration

- Administer as an intravenous infusion only.
- Do not administer as an intravenous push or bolus.
- Do not mix GAZYVA with other drugs.
- No incompatibilities between GAZYVA and polyvinylchloride (PVC) or non-PVC polyolefin bags and administration sets have been observed.

3 DOSAGE FORMS AND STRENGTHS

Injection: 1,000 mg/40 mL (25 mg/mL) clear, colorless to slightly brown solution in a single-dose vial.

4 CONTRAINDICATIONS

GAZYVA is contraindicated in patients with known hypersensitivity reactions (e.g., anaphylaxis) to obinutuzumab or to any of the excipients, or serum sickness with prior obinutuzumab use [see Warnings and Precautions (5.4)].

5 WARNINGS AND PRECAUTIONS

5.1 Hepatitis B Virus Reactivation

GAZYVA can cause Hepatitis B virus (HBV) reactivation. Hepatitis B virus (HBV) reactivation, in some cases resulting in fulminant hepatitis, hepatic failure, and death, can occur in patients treated with anti-CD20 antibodies such as GAZYVA. HBV reactivation has been reported in patients who are hepatitis B surface antigen (HBsAg) positive and also in patients who are HBsAg negative but are hepatitis B core antibody (anti-HBc) positive. Reactivation has also occurred in patients who appear to have resolved hepatitis B infection (i.e., HBsAg negative, anti-HBc positive, and hepatitis B surface antibody [anti-HBs] positive).

HBV reactivation is defined as an abrupt increase in HBV replication manifesting as a rapid increase in serum HBV DNA level or detection of HBsAg in a person who was previously HBsAg negative and anti-HBc positive. Reactivation of HBV replication is often followed by hepatitis, i.e., increase in transaminase levels and, in severe cases, increase in bilirubin levels, liver failure, and death.

Screen all patients for HBV infection by measuring HBsAg and anti-HBc before initiating treatment with GAZYVA. For patients who show evidence of hepatitis B infection (HBsAg positive [regardless of antibody status] or HBsAg negative but anti-HBc positive), consult healthcare providers with expertise in managing hepatitis B regarding monitoring and consideration for HBV antiviral therapy.

Monitor patients with evidence of current or prior HBV infection for clinical and laboratory signs of hepatitis or HBV reactivation during and for several months following treatment with GAZYVA. HBV reactivation has been reported for other CD20-directed cytolytic antibodies following completion of therapy.

In patients who develop reactivation of HBV while receiving GAZYVA, immediately discontinue GAZYVA and any concomitant chemotherapy and institute appropriate treatment. Resumption of GAZYVA in patients whose HBV reactivation resolves should be discussed with healthcare providers with expertise in managing hepatitis B. Insufficient data exist regarding the safety of resuming GAZYVA in patients who develop HBV reactivation.

5.2 Progressive Multifocal Leukoencephalopathy

John Cunningham (JC) virus infection resulting in progressive multifocal leukoencephalopathy (PML), which can be fatal, occurred in patients treated with GAZYVA for CLL and NHL. Consider the diagnosis of PML in any patient presenting with new onset or changes to preexisting neurologic manifestations. Evaluation of PML includes, but is not limited to, consultation with a neurologist, brain MRI, and lumbar puncture. Discontinue GAZYVA therapy and consider discontinuation or reduction of any concomitant chemotherapy or immunosuppressive therapy in patients who develop PML.

5.3 Infusion-Related Reactions

GAZYVA can cause severe and life-threatening infusion-related reactions (IRRs). Sixty-five percent of patients with CLL experienced a reaction to the first 1,000 mg of GAZYVA infused. Thirty-seven percent of patients with relapsed or refractory NHL and 60% of patients with previously untreated NHL experienced a reaction on Day 1 of GAZYVA infusion. In patients with CLL and NHL , IRRs have occurred within 24 hours of receiving GAZYVA. IRRs can also occur with subsequent infusions. Symptoms may include hypotension, tachycardia, dyspnea, and respiratory symptoms (e.g., bronchospasm, larynx and throat irritation, wheezing, laryngeal edema). The most frequently reported IRR symptoms in patients with CLL and NHL include nausea, fatigue, chest discomfort, dyspnea, dizziness, vomiting, diarrhea, rash, hypertension, hypotension, flushing, headache, pyrexia, and chills [see Adverse Reactions (6.1)].

In patients with LN, IRRs occurred predominantly during infusion of the first 1,000 mg. IRRs were generally mild to moderate and could be managed by the slowing or temporarily halting the infusion [see Dosage and Administration (2.6)]. Severe and life-threatening IRRs requiring symptomatic treatment were also reported. The most common IRR signs or symptoms reported in the REGENCY study included headache, nausea and vomiting. In the NOBILITY study, the most common IRR symptoms were pyrexia and tachycardia [see Adverse Reactions (6.2)].

Premedicate patients with acetaminophen, anti-histamine, and a glucocorticoid [see Dosage and Administration (2.4)]. Closely monitor patients during the entire infusion. Reduce infusion rate, interrupt infusion or permanently discontinue GAZYVA for IRRs based on severity [see Dosage and Administration (2.5)]. Institute medical management (e.g., glucocorticoids, epinephrine, bronchodilators, and/or oxygen) for IRRs as needed.

For patients with preexisting cardiac or pulmonary conditions, monitor more frequently throughout the infusion and the post-infusion period since they may be at greater risk of experiencing more severe reactions. Hypotension may occur as part of the IRR to GAZYVA. Consider withholding antihypertensive treatments for 12 hours prior to, during each GAZYVA infusion, and for the first hour after administration until blood pressure is stable. For patients at increased risk of hypertensive crisis, consider the benefits versus the risks of withholding their antihypertensive medication as is suggested here.

5.4 Hypersensitivity Reactions Including Serum Sickness

Hypersensitivity reactions have been reported in patients treated with GAZYVA. Signs of immediate-onset hypersensitivity included dyspnea, bronchospasm, hypotension, urticaria and tachycardia. Late-onset hypersensitivity diagnosed as serum sickness has also been reported, with symptoms that include chest pain, diffuse arthralgia and fever. Hypersensitivity reactions may be difficult to clinically distinguish from IRRs. However, hypersensitivity very rarely occurs with the first infusion and, when observed, often occurs after previous exposure.

If a hypersensitivity reaction is suspected during or after an infusion, stop the infusion and permanently discontinue treatment. GAZYVA is contraindicated in patients with known hypersensitivity reactions to GAZYVA, including serum sickness with prior GAZYVA use [see Contraindications (4)].

5.5 Tumor Lysis Syndrome

Tumor lysis syndrome (TLS), including fatal cases, has been reported in patients with CLL and NHL receiving GAZYVA. Patients with high tumor burden, high circulating lymphocyte count (> 25 × 10^9/L) or renal impairment are at greater risk for TLS.

In patients with CLL and NHL at risk for TLS, administer appropriate tumor lysis prophylaxis with anti-hyperuricemics (e.g., allopurinol or rasburicase) and hydration prior to the infusion of GAZYVA [see Dosage and Administration (2.4)]. During the initial days of GAZYVA treatment, monitor the laboratory parameters of patients considered at risk for TLS. For treatment of TLS, correct electrolyte abnormalities, monitor renal function and fluid balance, and administer supportive care, including dialysis as indicated. TLS is not identified as a risk in LN.

5.6 Serious, Including Fatal, Infections

Fatal and serious bacterial, fungal, and new or reactivated viral infections can occur during and following GAZYVA therapy. When GAZYVA is administered with chemotherapy followed by GAZYVA monotherapy as in the GALLIUM study, Grade 3 to 5 infections have been reported in up to 8% of patients during combination therapy, up to 13% of patients during monotherapy, and up to 8% of patients after treatment [see Adverse Reactions (6.1)].

Lupus Nephritis

In the pooled double-blind periods of REGENCY (Week 76) and NOBILITY (Week 52), the incidence of Grade 3-5 infections was 11% (22/200) in patients treated with GAZYVA and standard therapy compared to 9% (18/193) in patients receiving placebo and standard therapy, corresponding to an exposure-adjusted incidence rate (EAIR) of 8.9 and 7.9 per 100 patient years, respectively. The incidence of fatal infections was 1% (2/200) in patients treated with GAZYVA and 0.5% (1/193) in patients receiving placebo, corresponding to an EAIR of 0.8 and 0.4 per 100 patient years, respectively.

In 40 patients who crossed-over from placebo to GAZYVA and standard therapy at Week 76 in the REGENCY study and patients who continued treatment with GAZYVA and standard therapy, including additional treatment after Week 76, the EAIR of Grade 3-5 infections for the GAZYVA arm was 9.0 per 100 patient-years while the EAIR of fatal infections for the GAZYVA arm was 1.8 per 100 patient-years.

CLL and FL

In GALLIUM, more Grade 3 to 5 infections were reported in the recipients of GAZYVA and bendamustine (117/410 patients, 29%) as compared to GAZYVA plus CHOP or CVP (43/281 patients, 15%). More fatal infections were reported in patients treated with GAZYVA and bendamustine (3%), as compared to GAZYVA plus CHOP or CVP (< 1%), including during the monotherapy phase and after completion of treatment.

Do not administer GAZYVA to patients with an active infection. Patients with a history of recurring or chronic infections may be at increased risk of infection. In patients who develop a serious infection while receiving GAZYVA, immediately discontinue GAZYVA and institute appropriate treatment. Consider the risk and benefit of resuming treatment with GAZYVA following resolution of serious infections.

5.7 Neutropenia

Severe and life-threatening neutropenia, including febrile neutropenia, has been reported during treatment with GAZYVA. Monitor patients with Grade 3 to 4 neutropenia frequently with regular laboratory tests until resolution. Anticipate, evaluate, and treat any symptoms or signs of developing infection. Consider dose delays for Grade 3 or 4 neutropenia. Consider administration of granulocyte colony-stimulating factors (GCSF) in patients with Grade 3 or 4 neutropenia.

Neutropenia can also be of late onset (occurring more than 28 days after completion of treatment) and/or prolonged (lasting longer than 28 days). Patients with severe and long lasting (> 1 week) neutropenia are strongly recommended to receive antimicrobial prophylaxis until resolution of neutropenia to Grade 1 or 2. Consider antiviral and antifungal prophylaxis.

5.8 Thrombocytopenia

Severe and life-threatening thrombocytopenia has been reported during treatment with GAZYVA in combination with chemotherapy. Fatal hemorrhagic events have been reported in patients with NHL and CLL treated with GAZYVA in combination with chemotherapy, including during Cycle 1.

Monitor patients frequently for thrombocytopenia and hemorrhagic events, especially during the first cycle and if clinically indicated, evaluate laboratory coagulation parameters [see Warnings and Precautions (5.9)]. In patients with Grade 3 or 4 thrombocytopenia, monitor platelet counts more frequently until resolution and consider dose delays of GAZYVA and chemotherapy or dose reductions of chemotherapy. Transfusion of blood products (i.e., platelet transfusion) may be necessary. Consider withholding concomitant medications that may increase bleeding risk (platelet inhibitors, anticoagulants), especially during the first cycle.

5.9 Disseminated Intravascular Coagulation (DIC)

Fatal and severe DIC has been reported in patients receiving GAZYVA for treatment of CLL and NHL. The majority of DIC cases have involved changes in platelets and laboratory coagulation parameters following the first infusion, with spontaneous resolution usually occurring by Day 8. In some cases, DIC was associated with IRRs, TLS, or both [see Adverse Reactions (6.1)].

In patients with suspected DIC, evaluate potential causes, and monitor coagulation parameters, platelet counts, and for signs and symptoms of bleeding or thrombosis. Manage according to standard guidelines for DIC. Supportive care, including transfusion of blood products and other medical management, may be necessary.

5.10 Immunization

The safety and efficacy of immunization with live or attenuated viral vaccines during or following GAZYVA therapy have not been studied. Immunization with live virus vaccines is not recommended during treatment with GAZYVA and until B-cell recovery.

5.11 Embryo-Fetal Toxicity

Based on its mechanism of action and findings in animals, GAZYVA can cause B-cell depletion in infants exposed to obinutuzumab in-utero. Advise pregnant women of the potential risk to the fetus. Advise females of reproductive potential to use effective contraception while taking GAZYVA and for 6 months after the last dose [see Use in Specific Populations (8.1, 8.3)].

6 ADVERSE REACTIONS

The following clinically significant adverse reactions are described elsewhere in the labeling:

- Hepatitis B virus reactivation [see Warnings and Precautions (5.1)]
- Progressive multifocal leukoencephalopathy [see Warnings and Precautions (5.2)]
- Infusion-related reactions [see Warnings and Precautions (5.3)]
- Hypersensitivity reactions including serum sickness [see Warnings and Precautions (5.4)]
- Tumor lysis syndrome [see Warnings and Precautions (5.5)]
- Infections [see Warnings and Precautions (5.6)]
- Neutropenia [see Warnings and Precautions (5.7)]
- Thrombocytopenia [see Warnings and Precautions (5.8)]
- Disseminated intravascular coagulation [see Warnings and Precautions (5.9)]

6.1 Clinical Trials Experience

Because clinical trials are conducted under widely varying conditions, adverse reaction rates observed in the clinical trials of a drug cannot be directly compared to rates in the clinical trials of another drug and may not reflect the rates observed in practice.

Chronic Lymphocytic Leukemia

The data below are based on a safety population of 773 previously untreated patients with CLL in the CLL11 study. Patients were treated with chlorambucil alone, GAZYVA in combination with chlorambucil, or rituximab product in combination with chlorambucil. The Stage 1 analysis compared GAZYVA in combination with chlorambucil vs. chlorambucil alone and Stage 2 compared GAZYVA in combination with chlorambucil vs. rituximab product in combination with chlorambucil. Adverse reactions rates and laboratory abnormalities from the Stage 2 phase are presented below and are consistent with the rates in Stage 1. In addition to the adverse reactions observed in Stage 2, in Stage 1, back pain (5% vs. 2%), anemia (12% vs. 10%) and cough (10% vs. 7%) were observed at a higher incidence in the GAZYVA treated patients. The incidence of Grade 3 to 4 back pain (< 1% vs. 0%), cough (0% vs. < 1%) and anemia (5% vs. 4%) was similar in both treatment arms. With regard to laboratory abnormalities, in Stage 1 hyperkalemia (33% vs. 18%), creatinine increased (30% vs. 20%) and alkaline phosphatase increased (18% vs. 11%) were observed at a higher incidence in patients treated with GAZYVA with similar incidences of Grade 3 to 4 abnormalities between the two arms.

Patients received three 1,000 mg doses of GAZYVA on the first cycle and a single dose of 1,000 mg once every 28 days for 5 additional cycles in combination with chlorambucil (6 cycles of 28 days each in total). In the last 140 patients enrolled, the first dose of GAZYVA was split between day 1 (100 mg) and day 2 (900 mg) [see Dosage and Administration (2.2)]. In total, 81% of patients received all 6 cycles (of 28 days each) of GAZYVA-based therapy.

Adverse reactions in ≥ 10% of patients in the GAZYVA containing arm were infusion-related reactions, neutropenia, thrombocytopenia, and diarrhea. The most common Grade 3 to 4 adverse reactions (incidence ≥ 10%) in the GAZYVA containing arm were neutropenia, infusion-related reactions, and thrombocytopenia.

Table 7 Adverse Reactions (Incidence ≥ 5% and ≥ 2% Greater in the GAZYVA Arm) in Patients with CLL (Stage 2)
Body System Adverse Reactions | GAZYVA + Chlorambucil n = 336 |  | Rituximab product + Chlorambucil n = 321
Body System Adverse Reactions | All Grades % | Grades 3 to 4 % | All Grades % | Grades 3 to 4 %
Injury, Poisoning and Procedural Complications
Infusion-Related Reaction | 66 | 20 | 38 | 4
Blood and Lymphatic System Disorders [Adverse reactions reported under "Blood and lymphatic system disorders" reflect those reported by investigator as clinically significant.]
Neutropenia | 38 | 33 | 32 | 28
Thrombocytopenia | 14 | 10 | 7 | 3
Gastrointestinal Disorders
Diarrhea | 10 | 2 | 8 | < 1
Constipation | 8 | 0 | 5 | 0
General Disorders and Administration Site Conditions
Pyrexia | 9 | < 1 | 7 | < 1
Infections and Infestations
Nasopharyngitis | 6 | < 1 | 3 | 0
Urinary Tract Infection | 5 | 1 | 2 | < 1

Table 8 Post-Baseline Laboratory Abnormalities (Incidence ≥ 10% and ≥ 2% Greater in the GAZYVA Arm) in Patients with CLL (Stage 2)
Laboratory Abnormalities | GAZYVA + Chlorambucil n = 336 |  | Rituximab product + Chlorambucil n = 321
 | All Grades % | Grades 3 to 4 % | All Grades % | Grades 3 to 4 %
Hematology
Leukopenia | 84 | 35 | 62 | 16
Lymphopenia | 80 | 39 | 50 | 16
Neutropenia | 76 | 46 | 69 | 41
Thrombocytopenia | 48 | 13 | 40 | 8
Anemia | 39 | 10 | 37 | 10
Chemistry
Hypocalcemia | 37 | 3 | 32 | < 1
ALT increased | 28 | 2 | 21 | 1
AST increased | 27 | 2 | 21 | < 1
Hyponatremia | 26 | 7 | 18 | 2
Hypoalbuminemia | 23 | < 1 | 16 | < 1
Hypokalemia | 14 | 1 | 10 | < 1

Non-Hodgkin Lymphoma

GADOLIN Study

The GADOLIN study evaluated safety in 407 patients with relapsed or refractory NHL, including FL (81%), small lymphocytic lymphoma and marginal zone lymphoma (a disease for which GAZYVA is not indicated), who did not respond to or progressed within 6 months of treatment with rituximab product or a rituximab product-containing regimen. In the population of patients with FL, the profile of adverse reactions was consistent with the overall NHL population. Patients received either GAZYVA in combination with bendamustine (204 patients), followed by GAZYVA monotherapy in patients that had not progressed, or bendamustine alone (203 patients).

Patients randomized to the GAZYVA + bendamustine arm received three weekly 1,000 mg doses of GAZYVA in the first cycle and a single dose of 1,000 mg once every 28 days for 5 additional cycles, in combination with bendamustine 90 mg/m^2 intravenously on Days 1 and 2 in all 6 cycles. Patients who did not progress on the combination received a single 1,000 mg dose of GAZYVA monotherapy every two months until progression or for a maximum of two years. The control arm received bendamustine 120 mg/m^2 on Days 1 and 2 of each cycle for 6 cycles, with a cycle length of 28 days. In the GAZYVA arm, 78% of patients received 6 cycles of bendamustine and 82% received their full 6 cycles of GAZYVA; 72 (46%) of the 158 patients who began GAZYVA monotherapy received all planned doses. In the control arm, 72% of patients received 6 cycles of bendamustine.

Serious adverse reactions occurred in 45% of the GAZYVA arm and 37% of the bendamustine-only arm. Fatal adverse reactions within 90 days of treatment occurred in 3.4% and 2.5%, respectively. During treatment and follow-up combined, fatal adverse reactions occurred in 10% of GAZYVA recipients and in 7.4% of recipients of bendamustine alone, with infection and second primary malignancies being the leading causes.

Dose modification due to adverse reactions occurred in 50% of the GAZYVA arm and 42% of the control arm, and discontinuation of any study drug due to adverse reactions occurred in 20% and 17%, respectively.

Table 9 presents selected adverse reactions in GADOLIN. The most common adverse reactions (incidence ≥ 20%) in GAZYVA recipients included infusion-related reactions, fatigue, neutropenia, cough, upper respiratory tract infections, and musculoskeletal pain.

Table 9 Adverse Reactions (Incidence ≥ 10% and ≥ 2% Greater in the GAZYVA Arm) in Patients with Relapsed or Refractory NHL (GADOLIN)
Body System Adverse Reactions [Includes adverse reactions reported throughout study treatment and follow-up.] , [Includes grouped terms.] | GAZYVA + Bendamustine followed by GAZYVA monotherapy n = 204 |  | Bendamustine n = 203
Body System Adverse Reactions [Includes adverse reactions reported throughout study treatment and follow-up.] , [Includes grouped terms.] | All Grades % | Grades 3 to 5 % | All Grades % | Grades 3 to 5 %
Procedural Complications
Infusion-Related Reaction [Except where noted, individual events that meet the definition of "infusion-related reaction" are excluded from Table 9 above, as they are included in the grouped term "Infusion-Related Reaction".] | 67 | 11 | 63 | 5
General Disorders
Fatigue | 40 | 3 | 36 | 3
Pyrexia | 19 | 1 | 15 | 1
Blood and Lymphatic System Disorders
Neutropenia | 37 | 35 [Includes 1 fatal event.] | 29 | 27
Infections and Infestations
Upper Respiratory Tract Infection | 36 | 3 | 23 | 1
Respiratory Tract Infection, Unspecified | 14 | 1 | 8 | 0
Urinary Tract Infection | 13 | 3 | 7 | 0
Respiratory, Thoracic and Mediastinal Disorders
Cough | 31 | <1 | 21 | 0
Musculoskeletal and Connective Tissue Disorders
Musculoskeletal Pain | 28 | 1 | 20 | 0
Arthralgia | 12 | <1 | 5 | 0
Skin and Subcutaneous Tissue Disorders
Rash | 17 | <1 | 14 | <1
Pruritus | 11 | 0 | 6 | 0

Infusion-related reactions are defined as any related adverse reaction that occurred during or within 24 hours of infusion.

Fatigue includes fatigue, lethargy, asthenia.

Pyrexia includes pyrexia, hyperthermia, body temperature increased.

Cough includes cough, productive cough, upper-airway cough syndrome.

Neutropenia includes neutropenia, agranulocytosis, granulocytopenia, neutrophil count decreased.

Upper respiratory tract infection includes upper respiratory tract congestion, upper respiratory tract inflammation, upper respiratory fungal infection, rhinovirus infection, and all terms containing: upper respiratory tract infection, laryngitis, nasopharyngitis, pharyngitis, rhinitis, tonsillitis, and sinusitis with the exception of sinobronchitis.

Respiratory tract infection unspecified includes respiratory tract infection, respiratory tract infection viral, influenza, influenza-like illness, sinobronchitis, respiratory syncytial virus infection.

Urinary tract infection includes all terms containing: urinary tract infection, cystitis, pyelonephritis.

Musculoskeletal pain includes non-cardiac chest pain, bone pain, spinal pain, myalgia, back pain, neck pain, musculoskeletal discomfort, pain in extremity, and all terms containing "musculoskeletal pain".

Rash includes drug eruption, skin reaction, all terms containing "rash", urticaria, and selected terms containing "dermatitis".

Pruritus includes pruritus, pruritus generalized.

Other clinically relevant adverse reactions (incidence < 10% and ≥ 2% greater in the GAZYVA arm) included:

- Blood and lymphatic system disorders: febrile neutropenia (6%)
- Infection: sepsis (7%)

During GAZYVA monotherapy (158 patients), adverse reactions in ≥ 10% of patients included upper and lower respiratory tract infections, cough, neutropenia, musculoskeletal pain, fatigue, diarrhea, rash, and urinary tract infection.

Table 10 presents selected new or worsening laboratory abnormalities in the GADOLIN trial.

Table 10 New or Worsening Laboratory Abnormalities (Incidence ≥ 10% and ≥ 2% Greater in the GAZYVA Arm [Two percent difference in either any-grade or Grade 3 to 4 laboratory abnormalities.]) in Patients with Relapsed or Refractory NHL (GADOLIN)
Laboratory Abnormalities | GAZYVA + Bendamustine followed by GAZYVA monotherapy n = 204 |  | Bendamustine n = 203
Laboratory Abnormalities | All Grades % | Grades 3 to 4 % | All Grades % | Grades 3 to 4 %
Hematology
Lymphopenia | 97 | 92 | 96 | 84
Leukopenia | 84 | 47 | 87 | 34
Neutropenia | 76 | 53 | 75 | 42
Chemistry
Hypophosphatemia | 41 | 8 | 38 | 7
Hypocalcemia | 39 | 3 | 24 | 1
ALT/SGPT increased | 36 | 2 | 31 | 3
Alkaline phosphatase increased | 27 | 0 | 23 | 0
Hyperbilirubinemia | 21 | 2 | 17 | 2
Hyperkalemia | 20 | 3 | 18 | 0

In the GAZYVA monotherapy phase, new or worsening grade 3 or 4 abnormalities included neutropenia in 25% of patients (Grade 4, 10%) and lymphopenia in 23% (Grade 4, 5%).

GALLIUM Study

A randomized, open-label multicenter trial (GALLIUM) evaluated the safety of GAZYVA as compared to rituximab product in 1385 patients with previously untreated follicular lymphoma (86%) or marginal zone lymphoma (14%). Patients received chemotherapy (bendamustine, CHOP, or CVP) combined with either GAZYVA (691 patients) or rituximab product (694 patients), followed in responding patients by GAZYVA or rituximab product monotherapy every two months until disease progression or for a maximum of two years. The study excluded patients having an absolute neutrophil count (ANC) < 1500 / µL, platelets < 75,000 / µL, CLcr < 40 mL/min and, unless attributable to lymphoma, hepatic transaminases > 2.5 × upper limit of normal.

The median age was 60 (range: 23-88), 47% were male, 82% were white, and 97% had an ECOG performance status of 0 or 1. The chemotherapy was bendamustine in 59%, CHOP in 31% and CVP in 10% of patients. Following combination therapy, 624 patients (90%) in the GAZYVA arm and 612 patients (88%) in the rituximab product arm received monotherapy.

Serious adverse reactions occurred in 50% of patients on the GAZYVA arm and 43% of patients on the rituximab product arm. Fatal adverse reactions were reported during treatment in 3% in the GAZYVA arm and 2% in the rituximab product arm, most often from infections in the GAZYVA arm. During treatment and follow-up combined, fatal adverse reactions were reported in 5% of the GAZYVA arm and 4% of the rituximab product arm, with infections and second malignancies being leading causes. In the GAZYVA arm, fatal infections occurred in 2% of patients compared to < 1% in the rituximab product arm.

During combination therapy, 93% of patients received all treatment cycles in the GAZYVA arm, and 92% received all treatment cycles in the rituximab product arm. Of the responding patients who began monotherapy with GAZYVA or rituximab product, 76% and 73%, respectively, completed the full course. Dose modification due to adverse reactions occurred in 74% of the GAZYVA arm and 63% of the rituximab product arm throughout study treatment, and discontinuation of any study drug due to adverse reactions occurred in 18% and 15%, respectively.

Throughout treatment and follow-up, the most common adverse reactions (incidence ≥ 20%) observed at least 2% more in the GAZYVA arm included infusion-related reactions, neutropenia, upper respiratory tract infections, constipation and diarrhea (Table 11). Neutropenia, infusion-related reactions, febrile neutropenia and thrombocytopenia were the most common Grade 3 to 5 adverse reactions (incidence ≥ 5%) observed more frequently in the GAZYVA arm.

Table 11 Adverse Reactions (Incidence ≥ 10% and ≥ 2% Greater in the GAZYVA Arm) in Patients with Previously Untreated NHL (GALLIUM)
Body System Adverse Reactions [Includes adverse reactions reported throughout study treatment and follow-up.] , [Includes grouped terms.] | GAZYVA + chemotherapy followed by GAZYVA monotherapy n = 691 |  | Rituximab product + chemotherapy followed by rituximab product monotherapy n = 694
Body System Adverse Reactions [Includes adverse reactions reported throughout study treatment and follow-up.] , [Includes grouped terms.] | All Grades % | Grades 3 to 5 % | All Grades % | Grades 3 to 5 %
Injury, Poisoning and Procedural Complications
Infusion-Related Reaction [Except where noted, individual events that meet the definition of "infusion-related reaction" are excluded from Table 11 above, as they are already included in the grouped term "Infusion-Related Reaction". The most common individual terms within the grouped term "Infusion-Related Reaction" in decreasing order of frequency are nausea, chills, pyrexia and vomiting.] | 72 | 12 | 60 | 8
Blood and Lymphatic System Disorders
Neutropenia [Includes adverse reactions reported as infusion-related reactions.] | 53 | 49 | 47 | 41
Thrombocytopenia | 14 | 7 | 8 | 3
Infections and Infestations
Upper Respiratory Tract Infection | 50 | 3 | 43 | 1
Herpesvirus Infection | 18 | 3 | 14 | 1
Pneumonia | 14 | 7 | 12 | 6
Respiratory, Thoracic and Mediastinal Disorders
Cough | 35 | < 1 | 28 | < 1
Gastrointestinal Disorders
Constipation | 32 | < 1 | 29 | < 1
Diarrhea | 30 | 3 | 26 | 2
Nervous System Disorders
Headache | 18 | < 1 | 15 | < 1
Musculoskeletal and Connective Tissue Disorders
Arthralgia | 16 | 0 | 14 | < 1
Psychiatric Disorders
Insomnia | 15 | < 1 | 12 | < 1
Metabolism and Nutrition Disorders
Decreased Appetite | 14 | < 1 | 12 | < 1
Skin and Subcutaneous Tissue Disorders
Pruritus | 11 | < 1 | 9 | 0

Infusion-related reactions are defined as any related adverse reaction that occurred during or within 24 hours of infusion.

Neutropenia includes neutropenia, agranulocytosis, granulocytopenia, and neutrophil count decreased.

Febrile neutropenia includes febrile neutropenia, neutropenic infection, neutropenic sepsis, and febrile bone marrow aplasia.

Thrombocytopenia includes thrombocytopenia and platelet count decreased.

Upper respiratory tract infection includes upper respiratory tract congestion, upper respiratory tract inflammation, upper respiratory tract infection, rhinovirus infection, and all terms containing: laryngitis, nasopharyngitis, pharyngitis, rhinitis, tonsillitis, and sinusitis with the exception of sinobronchitis.

Herpesvirus infection includes all terms containing "herpes" or "varicella."

Pneumonia includes all terms containing "pneumonia," bacterial, pneumonia haemophilus, pneumonia pneumococcal, pneumonia fungal, pneumocystis jirovecii infection, lung infection, and lung infiltration.

Diarrhea includes diarrhea, defecation urgency, frequent bowel movement, and all terms containing "gastroenteritis".

Headache includes all terms containing "headache" and migraine.

Insomnia includes all terms containing "insomnia" and sleep disorder.

Pruritus includes pruritus and pruritus generalized.

During the monotherapy period, the common adverse reactions (incidence ≥ 10%) observed at least 2% more with GAZYVA were upper respiratory tract infection (40%), cough (23%), musculoskeletal pain (20%), neutropenia (19%), and herpesvirus infection (13%).

Table 12 summarizes treatment-emergent laboratory abnormalities during treatment and follow-up. The Grade 3 to 4 abnormalities reported at least 2% more in the GAZYVA arm were lymphopenia, leukopenia, neutropenia, thrombocytopenia, and hyperuricemia. Patients in the GAZYVA arm, as compared to the rituximab product arm, had higher incidences of Grade 4 neutropenia (38% vs. 30%, respectively), Grade 4 lymphopenia (33% vs. 22%), and Grade 4 leukopenia (17% vs. 12%).

Table 12 New or Worsening Laboratory Abnormalities (Incidence ≥ 10% and ≥ 2% Greater in the GAZYVA Arm) in Patients with Previously Untreated NHL (GALLIUM)
Laboratory Abnormalities [Includes lab abnormalities, reported throughout treatment and follow-up, that were new or worsening, or worsening from baseline unknown.] | GAZYVA+ chemotherapy followed by GAZYVA monotherapy n = 691 |  | Rituximab product + chemotherapy followed by rituximab product monotherapy n = 694
 | All Grades % | Grades 3 to 4 % | All Grades % | Grades 3 to 4 %
Hematology
Lymphopenia | 97 | 83 | 95 | 67
Leukopenia | 92 | 49 | 89 | 39
Neutropenia | 84 | 59 | 76 | 50
Thrombocytopenia | 68 | 11 | 50 | 4
Chemistry
ALT increased | 50 | 3 | 43 | 2
AST increased | 44 | 1 | 41 | 1
Hypophosphatemia | 36 | 5 | 33 | 5
Hypoalbuminemia | 33 | 1 | 25 | 1
Hypoproteinemia | 32 | 0 | 30 | 0
Hypocalcemia | 32 | 1 | 26 | 1
Hyperuricemia | 28 | 28 | 22 | 22
Hyponatremia | 26 | 4 | 20 | 3
Hyperkalemia | 23 | 1 | 17 | 1
Hypernatremia | 16 | < 1 | 13 | 0

In the monotherapy phase, new-onset Grade 3 or 4 neutropenia was reported in 21% of patients in the GAZYVA arm (Grade 4, 10%) and 17% of patients in the rituximab product arm (Grade 4, 9%).

GAZELLE Study

GAZELLE (NCT03817853) is a single-arm study designed to characterize the safety of GAZYVA administered as a shortened-duration infusion (approximately 90 minutes) in patients with previously untreated FL. All patients received GAZYVA at the standard infusion rate with premedication during Cycle 1. If no Grade 3 or higher IRR occurred with any infusion during Cycle 1, GAZYVA was administered over approximately 90 minutes in Cycle 2 and subsequent cycles. The primary safety measure was the proportion of patients who experienced Grade 3 or higher IRRs with the 90-minute infusion at Cycle 2. GAZYVA was administered in combination with CHOP, CVP or bendamustine for 6 to 8 cycles (induction), followed by monotherapy for up to 2 years.

Of the 113 patients treated with GAZYVA, 99 (88%) received the 90-minute infusion starting in Cycle 2. In total, 97% of patients who received GAZYVA at either a standard or shorter infusion duration received premedication in Cycle 2. IRRs were observed in 63% of patients throughout induction (including IRRs observed after standard-duration infusion). In cycle 1, 58% of patients developed IRRs with the standard infusion rate (Grade ≥3 IRR, 5%). Of the patients who received the 90-minute infusion, 10% had IRRs of any grade in Cycle 2, with 8% and 2% of patients having a Grade 1 IRR or Grade 2 IRR, respectively. Following Cycle 2, one (1%) patient experienced a Grade 3 IRR, which occurred after the 90-minute infusion at Cycle 5.

Lupus Nephritis

The data below reflects exposure to GAZYVA administered intravenously in patients with ISN/RPS 2003 Class III or IV with or without concomitant Class V lupus nephritis in the REGENCY and NOBILITY studies, up to week 76.

REGENCY (NCT04221477) is a Phase III study which included 136 patients treated with GAZYVA plus standard therapy consisting of mycophenolate mofetil (MMF) and corticosteroids [see Clinical Studies (14.3)].

NOBILITY (NCT02550652) is a Phase II study which included 64 patients treated with GAZYVA plus standard therapy consisting of MMF/mycophenolic acid (MPA) and corticosteroids.

The most common adverse reactions (incidence ≥ 5% in the GAZYVA arm) were upper respiratory tract infection, COVID-19, urinary tract infection, bronchitis, pneumonia, infusion related reactions and neutropenia.

The most common serious adverse reactions in the GAZYVA arm were: COVID-19 (11 patients [5.5%]), pneumonia (9 patients [4.5%]), neutropenia (7 patients [3.5%]), urinary tract infections (5 patients [2.5%]) and infusion-related reactions (1 patient [0.5%]). No serious adverse reactions were reported for bronchitis, herpes simplex and upper respiratory tract infections. Two fatal adverse reactions of COVID-19 were reported in the GAZYVA arm.

Adverse reaction rates are presented in Table 13.

Table 13 Adverse Reactions in Adults with Active Lupus Nephritis Treated with GAZYVA Versus Placebo (≥ 2% Greater in the GAZYVA Arm) in REGENCY and NOBILITY Studies
Body System Adverse Reactions | GAZYVA + standard therapy n = 200 |  | Placebo + standard therapy n = 193
Body System Adverse Reactions | All Grades (%) | Grades 3-5(%) | All Grades (%) | Grades 3-5 (%)
Infections and Infestations
Upper Respiratory Tract Infection | 29 | 0 | 24 | 0
COVID-19 | 23 | 5 [Includes 2 fatal events in the GAZYVA arm and 1 fatal event in the placebo arm] | 16 | 0.5
Urinary Tract Infection | 21 | 3 | 18 | 4
Bronchitis | 14 | 0 | 8 | 0.5
Pneumonia | 10 | 2 | 6 | 2
Herpes Simplex | 3 | 0 | 0 | 0
Injury, Poisoning and Procedural Complications
Infusion Related Reaction | 14 | 2 | 10 | 0.5
Blood and Lymphatic System Disorders
Neutropenia | 14 | 7 | 6 | 0.5

Specific Adverse Reactions

Infusion-Related Reactions

Chronic Lymphocytic Leukemia

The incidence of IRRs in the CLL11 study was 65% with the first infusion of GAZYVA. The incidence of Grade 3 or 4 IRRs was 20% with 7% of patients discontinuing therapy. The incidence of reactions with subsequent infusions was 3% with the second 1,000 mg and < 1% thereafter. No Grade 3 or 4 IRRs were reported beyond the first 1,000 mg infused.

Of the first 53 patients receiving GAZYVA in CLL11, 47 (89%) experienced an IRR. After this experience, study protocol modifications were made to require pre-medication with a corticosteroid, antihistamine, and acetaminophen. The first dose was also divided into two infusions (100 mg on day 1 and 900 mg on day 2). For the 140 patients for whom these mitigation measures were implemented, 74 patients (53%) experienced a reaction with the first 1,000 mg (64 patients on day 1, 3 patients on day 2, and 7 patients on both days) and < 3% thereafter [see Dosage and Administration (2.2)].

Non-Hodgkin Lymphoma

Overall, 67% of patients in the GADOLIN study experienced an IRR (all grades) during treatment with GAZYVA in combination with bendamustine. The incidence of Grade 3 to 4 IRRs in GADOLIN was 11%. In Cycle 1, the incidence of IRRs (all grades) was 53% in patients receiving GAZYVA in combination with bendamustine of which 34 (9%) were Grade 3 to 4 in severity. In patients receiving GAZYVA in combination with bendamustine, the incidence of IRRs was highest on Day 1 (37%), and gradually decreased on Days 2, 8 and 15 (23%, 6% and 4%, respectively).

During Cycle 2, the incidence of IRRs was 24% in patients receiving GAZYVA in combination with bendamustine and decreased with subsequent cycles.

During GAZYVA monotherapy in GADOLIN, IRRs (all grades) were observed in 8% of patients. One Grade 3 and no Grade 4 IRRs were reported during GAZYVA monotherapy.

Overall, 2% of patients in GADOLIN experienced an IRR leading to discontinuation of GAZYVA.

In GALLIUM, 72% of patients in the GAZYVA treated arm experienced an IRR (all grades). The incidence of Grade 3 to 4 IRRs for these patients was 12%. In Cycle 1, the incidence of IRRs (all grades) was 62% in the GAZYVA treated arm with Grade 3 to 4 IRRs reported in 10%. The incidence of IRRs (all grades) was highest on Day 1 (60%) and decreased on Days 8 and 15 (9% and 6%, respectively).

During Cycle 2, the incidence of IRRs (all grades) in the GAZYVA treated arm was 13% and decreased with subsequent cycles.

During GAZYVA monotherapy treatment in GALLIUM, IRRs (all grades) were observed in 9% of patients.

Overall, 1% of patients in GALLIUM experienced an IRR leading to discontinuation of GAZYVA.

In GAZELLE, 10% of patients with FL experienced IRRs of any grade at Cycle 2 when GAZYVA was administered over approximately 90 minutes.

Lupus Nephritis

In the pooled REGENCY and NOBILITY studies, infusion-related reactions (IRRs) were reported in 14% of patients in the GAZYVA arm versus 10% of patients in the placebo arm. IRRs in both arms were predominantly Grade 1-2 and occurred during or after the first infusion. Grade 3-4 IRRs were reported in 1.5% of patients in the GAZYVA arm vs 0.5% of patients in the placebo arm. All Grade 3-4 events occurred during or after either the first or second infusion.

The incidence of IRRs in the GAZYVA arm decreased from 11% during the first infusion to 3% during the second infusion, decreasing further with subsequent infusions to 0.5% during the sixth infusion. The severity of IRRs in the GAZYVA arm also decreased with subsequent infusions with 1% patients reporting Grade 3-4 IRRs during the first infusion and 0.5% patients reporting Grade 3-4 IRRs during the second infusion. In subsequent infusions all IRRs were Grade 1-2 in severity. No Grade 5 IRRs were reported [see Warnings and Precautions (5.3)].

In the REGENCY study, most common IRR signs or symptoms included headache, nausea and vomiting. In the NOBILITY study, the most common IRR symptoms were pyrexia and tachycardia.

Neutropenia

Chronic Lymphocytic Leukemia

The incidence of neutropenia reported as an adverse reaction in CLL11 was 38% in the GAZYVA treated arm and 32% in the rituximab product treated arm, with the incidence of serious adverse reactions being 1% and < 1%, respectively (Table 7). Cases of late-onset neutropenia (occurring 28 days after completion of treatment or later) were 16% in the GAZYVA treated arm and 12% in the rituximab product treated arm.

Non-Hodgkin Lymphoma

The incidence of neutropenia in GADOLIN was higher in the GAZYVA plus bendamustine arm (37%) compared to the arm treated with bendamustine alone (30%). Cases of prolonged neutropenia (3%) and late onset neutropenia (8%) were also reported in the GAZYVA plus bendamustine arm. The incidence of neutropenia was higher during treatment with GAZYVA in combination with bendamustine (30%) compared to the GAZYVA monotherapy treatment phase (13%).

The incidence of neutropenia in GALLIUM was higher in the GAZYVA treated arm (53%) compared to the rituximab product treated arm (47%). Cases of prolonged neutropenia (1%) and late onset neutropenia (4%) were also reported in the GAZYVA treated arm. The incidence of neutropenia was higher during treatment with GAZYVA in combination with chemotherapy (45%) compared to the GAZYVA monotherapy treatment phase (20%).

Lupus Nephritis

In the pooled REGENCY and NOBILITY studies, neutropenia and related adverse reactions (i.e., leukopenia, lymphopenia, lymphocyte count decreased, febrile neutropenia, and neutrophil count decreased) were reported in 14% of patients in the GAZYVA arm versus 6% of patients in the placebo arm. Grade 3-4 neutropenia was reported in 7% of patients treated with GAZYVA versus 0.5% of patients in the placebo arm. Neutropenia and related adverse reactions resolved/improved spontaneously or with use of granulocyte colony-stimulating factors in 96% of patients [see Warnings and Precautions (5.7)].

Infection

Chronic Lymphocytic Leukemia

The incidence of infections was similar between GAZYVA and rituximab product treated arms. Thirty-eight percent of patients in the GAZYVA treated arm and 37% in the rituximab product treated arm experienced an infection, with Grade 3 to 4 rates being 11% and 13%, respectively. Fatal events were reported in 1% of patients in both arms.

Non-Hodgkin Lymphoma

The incidence of infection in GADOLIN was 68% in the GAZYVA plus bendamustine arm and 59% in the bendamustine arm, with Grade 3 to 4 events reported in 20% and 16%, respectively. Fatal events were reported in 3% of patients in the GAZYVA plus bendamustine arm and 3% in the bendamustine arm.

The incidence of infections in GALLIUM was 82% in the GAZYVA treated arm and 73% in the rituximab product treated arm, with Grade 3 to 4 events reported in 21% and 17%, respectively. In the GAZYVA arm, fatal infections occurred in 2% of patients compared to <1% in the rituximab product arm.

The incidence of Grade 3 to 4 infections in the GAZYVA and rituximab product treated arms was lower in patients receiving GCSF prophylaxis (14%; 16%) compared with patients not receiving GCSF prophylaxis (24%; 18%). The incidence of fatal infections in patients receiving GCSF prophylaxis in the GAZYVA and rituximab product treated arms was 2% and 0%, respectively, and was 2% and < 1% in patients not receiving GCSF prophylaxis.

Lupus Nephritis

In the pooled REGENCY and NOBILITY studies, infections were reported in 72% of patients in the GAZYVA arm versus 62% of patients in the placebo arm. The most frequently reported infections were upper and lower respiratory tract infections. Grade 3-5 infections were reported in 11% of patients in the GAZYVA arm versus 10% of patients in the placebo arm. Fatal infection events were reported in 1% of patients in the GAZYVA arm versus 0.5% of patients in the placebo arm [see Warnings and Precautions (5.6)].

Thrombocytopenia

Chronic Lymphocytic Leukemia

The overall incidence of thrombocytopenia reported as an adverse reaction was higher in the GAZYVA treated arm (14%) compared to the rituximab product treated arm (7%), with the incidence of Grade 3 to 4 events being 10% and 3%, respectively (Table 7). The difference in incidences between the treatment arms is driven by events occurring during the first cycle. The incidence of thrombocytopenia (all grades) in the first cycle was 11% in the GAZYVA and 3% in the rituximab product treated arms, with Grade 3 to 4 rates being 8% and 2%, respectively. Four percent of patients in the GAZYVA treated arm experienced acute thrombocytopenia (occurring within 24 hours after the GAZYVA infusion).

The overall incidence of hemorrhagic events and the number of fatal hemorrhagic events were similar between the treatment arms, with 3 in the rituximab product and 4 in the GAZYVA treated arms. However, all fatal hemorrhagic events in patients treated with GAZYVA occurred in Cycle 1.

Non-Hodgkin Lymphoma

The incidence of thrombocytopenia in GADOLIN was lower in the GAZYVA plus bendamustine arm (15%) compared to the arm treated with bendamustine alone (25%). The incidence of hemorrhagic events in GAZYVA plus bendamustine treated patients compared to bendamustine alone was 12% and 11%, respectively. Grade 3 to 4 hemorrhagic events were similar in both treatment arms (4% in the GAZYVA plus bendamustine arm and 2% in the bendamustine arm).

In GALLIUM, thrombocytopenia was reported as an adverse reaction in 14% of the GAZYVA treated arm and 8% of the rituximab product treated arm, with the incidence of Grade 3 to 4 events being 7% and 3%, respectively. The difference in incidences between the treatment arms is driven by events occurring during the first cycle. The incidence of thrombocytopenia (all grades) in the first cycle was 9% in the GAZYVA and 3% in the rituximab product treated arms, with Grade 3 to 4 rates being 5% and 1%, respectively. In GALLIUM, both treatment arms had a 12% overall incidence of hemorrhagic events and a < 1% incidence of fatal hemorrhagic events.

Disseminated Intravascular Coagulation

In GALLIUM, DIC was reported as an adverse reaction in 0.3% of the GAZYVA treated patients. All events occurred within 1-2 days after the first infusion.

Tumor Lysis Syndrome

The incidence of Grade 3 or 4 tumor lysis syndrome in GAZYVA treated patients was 2% in CLL11, 0.5% in GADOLIN and 0.9% in GALLIUM.

Musculoskeletal Disorders

Chronic Lymphocytic Leukemia

Adverse reactions related to musculoskeletal disorders (all events from the body system), including pain, have been reported in the GAZYVA treated arm with higher incidence than in the rituximab product treated arm (18% vs. 15%).

Non-Hodgkin Lymphoma

In GADOLIN, adverse reactions related to musculoskeletal disorders (all events from the body system), including pain, have been reported in the GAZYVA plus bendamustine treated arm with higher incidence than in the bendamustine alone arm (44% vs. 30%).

In GALLIUM, musculoskeletal disorders were reported in 54% of patients in the GAZYVA treated arm and 49% of patients in the rituximab product treated arm.

Liver Enzyme Elevations

Hepatic enzyme elevations have occurred in CLL patients who received GAZYVA in clinical trials and had normal baseline hepatic enzyme levels (AST, ALT and ALP). The events occurred most frequently within 24–48 hours of the first infusion. In some patients, elevations in liver enzymes were observed concurrently with IRRs or tumor lysis syndrome. In the CLL11 study, there was no clinically meaningful difference in overall hepatotoxicity adverse reactions between all arms (4% of patients in the GAZYVA treated arm). Medications commonly used to prevent IRRs (e.g., acetaminophen) may also be implicated in these events. Monitor liver function tests during treatment, especially during the first cycle. Consider treatment interruption or discontinuation for hepatotoxicity.

Gastrointestinal Perforation

Cases of gastrointestinal perforation have been reported in patients receiving GAZYVA, mainly in NHL.

Worsening of Pre-existing Cardiac Conditions

Fatal cardiac events have been reported in patients treated with GAZYVA.

6.2 Postmarketing Experience

The following adverse reactions have been identified during postapproval use of GAZYVA. Because these reactions are reported voluntarily from a population of uncertain size, it is not always possible to reliably estimate their frequency or establish a causal relationship to drug exposure.

- Immune/Autoimmune Events: Serum sickness

8 USE IN SPECIFIC POPULATIONS

8.1 Pregnancy

Risk Summary

Based on findings from animal studies and its mechanism of action, GAZYVA can cause fetal B-cell depletion [see Clinical Pharmacology (12.1)]. There are no data with GAZYVA use in pregnant women to inform a drug-associated risk. Monoclonal antibodies are transferred across the placenta. In animal reproduction studies, weekly intravenous administration of obinutuzumab to pregnant cynomolgus monkeys from day 20 of pregnancy until parturition which includes the period of organogenesis at doses with exposures up to 2.4 times the exposure at the clinical dose of 1,000 mg monthly produced opportunistic infections and immune complex mediated hypersensitivity reactions. No embryo-toxic or teratogenic effects were observed in the monkeys (see Data). Advise pregnant women of the potential risk to the fetus.

The background risk of major birth defects and miscarriage for the indicated population is unknown; however, the estimated background risk in the U.S. general population of major birth defects is 2% to 4% and of miscarriage is 15% to 20% of clinically recognized pregnancies.

Clinical Considerations

Disease-Associated Maternal and/or Embryo/Fetal Risk

Pregnant women with systemic lupus erythematosus (SLE) are at increased risk of adverse pregnancy outcomes, including worsening of the underlying disease, premature birth, miscarriage, and intrauterine growth restriction. Maternal LN increases the risk of hypertension and preeclampsia/eclampsia. Passage of maternal autoantibodies across the placenta may result in adverse neonatal outcomes, including neonatal lupus and congenital heart block.

Fetal/Neonatal Adverse Reactions

GAZYVA is likely to cause fetal B-cell depletion (see Data). Avoid administering live vaccines to neonates and infants exposed to GAZYVA in utero until B-cell recovery occurs [see Warnings and Precautions (5.11) and Clinical Pharmacology (12.2)].

Data

Animal Data

In a pre- and post-natal development study, pregnant cynomolgus monkeys received weekly intravenous doses of 25 or 50 mg/kg obinutuzumab from day 20 of pregnancy until parturition, which includes the period of organogenesis. The high dose results in an exposure (AUC) that is 2.4 times the exposure in patients with CLL at the recommended label dose. There were no embryo-toxic or teratogenic effects in animals. Secondary opportunistic infections, immune complex mediated hypersensitivity reactions, or a combination of both were observed in exposed dams. When first measured on day 28 postpartum, obinutuzumab was detected in offspring at levels in the range of maternal serum levels on the same day, and B-cells were completely depleted. The B-cell counts returned to normal levels, and immunologic function was restored within 6 months after birth.

8.2 Lactation

Risk Summary

There is no information regarding the presence of GAZYVA in human milk, the effects on the breastfed child, or the effects on milk production. However, low levels of obinutuzumab were present in the milk of lactating cynomolgus monkeys [see Data]. Human IgG is known to be present in human milk. Because of the potential of serious adverse reactions in the breastfed child, advise women not to breastfeed during treatment with GAZYVA and for 6 months after the last dose.

Data

Obinutuzumab was measured in the milk of lactating cynomolgus monkeys on day 28 postpartum after weekly intravenous administration from day 20 of pregnancy until parturition. Concentrations in milk were approximately 0.04% and 0.13% of concentrations in maternal serum in the 25 and 50 mg/kg groups, respectively.

8.3 Females and Males of Reproductive Potential

GAZYVA can cause fetal harm when administered to a pregnant woman [see Use in Specific Populations (8.1)].

Contraception

Females

Advise females of reproductive potential to use effective contraception during treatment with GAZYVA and for 6 months after the last dose.

8.4 Pediatric Use

The safety and effectiveness of GAZYVA in pediatric patients have not been established.

8.5 Geriatric Use

Chronic Lymphocytic Leukemia

Of 336 patients with previously untreated CLL who received GAZYVA in combination with chlorambucil, 81% were 65 years and older, while 46% were 75 and older. Of the patients 75 years and older, 46% experienced serious adverse reactions and 7% experienced adverse reactions leading to death. Of the patients younger than 75, 33% experienced a serious adverse reaction and 2% an adverse reaction leading to death. No significant differences in efficacy were observed between younger and older patients [see Clinical Studies (14.1)].

Non-Hodgkin Lymphoma

Of 204 patients in GADOLIN with relapsed or refractory NHL treated with GAZYVA plus bendamustine, 44% were 65 and over, while 14% were 75 and over. In patients 65 and over, 55% of patients experienced serious adverse reactions and 28% experienced adverse reactions leading to treatment withdrawal while in patients under 65, 37% and 14% experienced serious adverse reactions and adverse reactions leading to treatment withdrawal, respectively. No clinically meaningful differences in efficacy were observed between these patients and younger patients in GADOLIN.

Of the 691 patients in GALLIUM treated with GAZYVA plus chemotherapy as first-line therapy, 33% were 65 and over, while 7% were 75 and over. Of patients 65 and over, 63% experienced serious adverse reactions and 26% experienced adverse reactions leading to treatment withdrawal, while in patients under 65, 43% experienced serious adverse reactions and 13% had an adverse reaction leading to treatment withdrawal. No clinically meaningful differences in efficacy were observed between these patients and younger patients in GALLIUM.

Lupus Nephritis

Clinical studies of GAZYVA in patients with active LN did not include sufficient numbers of patients aged 65 years and older (1 patient) to determine whether they respond differently from younger adult patients.

10 OVERDOSAGE

There has been no experience with overdose in human clinical trials. For patients who experience overdose, treatment should consist of immediate interruption or reduction of GAZYVA and supportive therapy.

11 DESCRIPTION

Obinutuzumab is a humanized anti-CD20 monoclonal antibody of the IgG1 subclass. It recognizes a specific epitope of the CD20 molecule found on B cells. The molecular mass of the antibody is approximately 150 kDa.

GAZYVA (obinutuzumab) injection is produced by mammalian cell (CHO) suspension culture. GAZYVA was engineered to have reduced fucose content as compared to a typical IgG1 produced in CHO cells. GAZYVA is a sterile, clear, colorless to slightly brown, preservative-free liquid concentrate for intravenous use. GAZYVA is supplied at a concentration of 25 mg/mL in 1,000 mg single-dose vials. Each vial contains in 40 mL: 1,000 mg obinutuzumab, L-histidine (57.6 mg), L-histidine hydrochloride monohydrate (89.6 mg), trehalose dihydrate (3632 mg), and poloxamer 188 (8 mg). The pH is 6.0.

12 CLINICAL PHARMACOLOGY

12.1 Mechanism of Action

Obinutuzumab is a monoclonal antibody that targets the CD20 antigen expressed on the surface of pre-B and mature B lymphocytes. Upon binding to CD20, obinutuzumab mediates B-cell lysis through (1) engagement of immune effector cells, (2) by directly activating intracellular death signaling pathways (direct cell death), and/or (3) activation of the complement cascade. The immune effector cell mechanisms include antibody-dependent cellular cytotoxicity (ADCC) and antibody-dependent cellular phagocytosis.

As an antibody with reduced fucose content, obinutuzumab induces greater ADCC activity than rituximab in vitro using human cancer cell lines. Obinutuzumab also demonstrated an increased ability to induce direct cell death when compared to rituximab. Obinutuzumab binds to FcγRIII using purified proteins with a higher affinity than rituximab. Obinutuzumab and rituximab bind with similar affinity to overlapping epitopes on CD20.

12.2 Pharmacodynamics

In patients with CLL, GAZYVA caused CD19 B-cell depletion (defined as CD19 B cell counts < 0.07 × 10^9/L). Initial CD19 B cell recovery was observed in some patients approximately 9 months after the last GAZYVA dose. At 18 months of follow-up, some patients remain B cell depleted.

Although the depletion of B cells in the peripheral blood is a measurable pharmacodynamic effect, it is not directly correlated with the depletion of B-cells in solid organs or in malignant deposits. B cell depletion has not been shown to be directly correlated to clinical response.

In patients with LN (REGENCY study), total peripheral CD19+ B cell levels below the defined threshold of 10 cells/µl were achieved in 99% of patients treated with GAZYVA by Week 4 after treatment initiation and remained below this threshold in 95% of patients at Week 76.

Reductions in circulating naive B, memory B, and plasmablasts/plasma cells were observed by Week 4 and remained low through Week 76 after treatment initiation.

Treatment with GAZYVA led to improvements in complement (C3 and C4) and anti-double-stranded DNA antibodies (anti-dsDNA) by Week 4 and Week 12, respectively. These changes were sustained through Week 76.

In patients with low C3 at baseline, normalization of C3 levels occurred in 49% (by Week 12) and in 62% (by Week 76) of patients receiving GAZYVA compared to 33% and 29%, respectively, in the placebo group. In patients with low C4 at baseline, normalization of C4 levels occurred in 75% (by Week 12) and in 88% (by Week 76) of patients receiving GAZYVA compared to 55% and 55%, respectively, in the placebo group. Among patients with positive anti-dsDNA at baseline, 32% and 56% of patients treated with GAZYVA seroconverted by Week 4 and Week 76, respectively, compared with 16% and 16% of patients receiving placebo.

The clinical relevance of the above mentioned pharmacodynamic biomarkers has not been established.

Cardiac Electrophysiology

The potential effects of GAZYVA on the QTc interval have not been studied.

12.3 Pharmacokinetics

The pharmacokinetic parameters of obinutuzumab after 100 mg on day 1 and 900 mg on day 2 of Cycle 1, 1,000 mg on day 8 and 15 of Cycle 1, and 1,000 mg on day 1 of Cycles 2-6 for CLL; after 1,000 mg on day 1, 8 and 15 of Cycle 1, 1,000 mg on day 1 of Cycles 2-6 or Cycles 2-8, and then 1,000 mg every 2 months for up to 2 years for NHL; 1,000 mg on day 1, week 2, 24, 26 and every 6 months for up to 76 Weeks for LN are provided in Table 14. The dosing regimen is within the linear pharmacokinetic behavior of obinutuzumab.

Table 14 Obinutuzumab Pharmacokinetic Parameters
PK Measure | CLL [Induction Cycle 6 of a 28-day cycle;] | Relapsed or refractory FL | First line FL in combination with chemotherapy |  | LN [Steady state values]
PK Measure | CLL [Induction Cycle 6 of a 28-day cycle;] | Relapsed or refractory FL | GAZYVA + Bendamustine | GAZYVA + CHOP or CVP [Induction Cycle 8 of a 21-day cycle.] | LN [Steady state values]
Cmax, µg/mL | 466.3 (35) | 553.5 (32) | 513.4 (28) | 676.4 (30) | 463 (18)
Ctrough, µg/mL | 192.5 (78) | 295 (56) | 255 (46) | 395 (44) | 0.91 (752)
AUC, µg/mL*day | 8701 (51) | 11362 (41) | 10088 (35) | 10723 (37) | 8770 (38)
Results are presented as geometric mean (% Coefficient of Variation).

Distribution and Elimination

CLL and NHL

The elimination of obinutuzumab is comprised of a linear clearance pathway and a time-dependent non-linear clearance pathway. As GAZYVA treatment progresses, the impact of the time-dependent pathway diminishes in a manner suggesting target-mediated drug disposition (TMDD) and saturation of the TMDD at the end of the treatment cycle at the proposed clinical dosing regimen. The distribution and elimination parameters of obinutuzumab in patients with CLL and NHL are provided in Table 15.

Table 15 Distribution and Elimination Parameters of Obinutuzumab
 | CLL | NHL
Distribution
Volume of Distribution [At steady state.] , L | 4.1 (20) | 4.3 (21)
Elimination
Terminal Half-life, days | 25.5 (48) | 35.3 (35)
Clearance, L/day | 0.11 (53) | 0.08 (41)
Parameters are presented as geometric mean (% Coefficient of Variation).

LN

The steady state clearance of obinutuzumab was approximately 0.13 L/day with a median elimination t1/2 of 22.4 days.

GAZYVA elimination comprises two parallel pathways, a linear clearance pathway and a non-linear clearance pathway, which changes as a function of time. The time-varying clearance decreases with time with an exponential decay coefficient, likely related to CD20 target reduction and proteinuria improvement over time, and a time-independent clearance related to the endogenous catabolic processes of IgG.

Specific Populations

CLL and NHL

Age (median [range]: 63 [22, 89] years) and baseline creatinine clearance (CLcr) (median [range] 84 [22, > 120] mL/min) did not affect the pharmacokinetics of GAZYVA. In patients with CLcr ≤ 30 mL/min, the pharmacokinetics of GAZYVA was unaffected. GAZYVA has not been studied in patients with hepatic impairment.

The volume of distribution and steady-state clearance increased with body weight; however, the expected change in exposure does not warrant a dosage modification.

LN

The population pharmacokinetic analysis of GAZYVA showed that creatinine clearance (CLcr) (median [range] 108 [28.9 - 282 mL/min]) does not affect the pharmacokinetics in patients with LN. The pharmacokinetics of obinutuzumab in patients with mild or moderate renal impairment were similar to those in patients with normal kidney function. The safety and efficacy of GAZYVA in patients with severe renal impairment has not been formally studied.

12.6 Immunogenicity

As with all therapeutic proteins, there is potential for immunogenicity. The detection of antibody formation is highly dependent on the sensitivity and specificity of the assay. Additionally, the observed incidence of anti-drug antibody (ADA) (including neutralizing antibody) positivity in an assay may be influenced by several factors including assay methodology, sample handling, timing of sample collection, concomitant medications, and underlying disease. For these reasons, comparison of the incidence of anti-drug antibodies in the studies described below with the incidence of anti-drug antibodies in other studies or to other products may be misleading.

Seven percent (18/271) of patients with CLL tested positive for anti-GAZYVA antibodies at one or more time points in CLL11. No patients developed anti-GAZYVA antibodies during or following GAZYVA treatment in GADOLIN, while 1 patient (1/564, 0.2%) developed anti-GAZYVA antibodies in GALLIUM. Neutralizing activity of anti-GAZYVA antibodies was not assessed.

In GAZYVA-treated patients in the LN studies, a total of 12 out of 200 (6%) had at least one ADA-positive sample recorded at any time during the studies. Six (3%) subjects had ADA-positive samples recorded at baseline in which two patients remained ADA-positive throughout the studies, one patient had a single post-baseline sample that was ADA-positive, and three patients had post-baseline samples that were all ADA-negative. Six (3%) patients with ADA-negative samples at baseline had a positive ADA titer post-baseline (treatment-induced ADA). None of the 12 patients with positive ADA titers at any time during the treatment period experienced an IRR or hypersensitivity reaction during the studies. Neutralizing activity of anti-GAZYVA antibodies was not assessed.

Because of the low occurrence of anti-drug antibodies, the effect of these antibodies on the pharmacokinetics, pharmacodynamics, safety and/or effectiveness of GAZYVA is unknown.

13 NONCLINICAL TOXICOLOGY

13.1 Carcinogenesis, Mutagenesis, Impairment of Fertility

No carcinogenicity or genotoxicity studies have been conducted with obinutuzumab.

No specific studies have been conducted to evaluate potential effects on fertility; however, no adverse effects on male or female reproductive organs were observed in the 26-week repeat-dose toxicity study in cynomolgus monkeys.

14 CLINICAL STUDIES

14.1 Chronic Lymphocytic Leukemia

The efficacy of GAZYVA was evaluated in a three-arm, open-label, active-controlled, randomized, multicenter trial (CLL11; NCT01010061) in 781 patients with previously untreated CD20+ CLL requiring treatment who had coexisting medical conditions or reduced renal function as measured by creatinine clearance (CLcr) < 70 mL/min. Patients with CLcr < 30 mL/min, active infections, positive hepatitis B (HBsAg or anti-HBc positive; patients positive for anti-HBc could be included if hepatitis B viral DNA was not detectable) and hepatitis C serology, or immunization with live virus vaccine within 28 days prior to randomization were excluded from the trial. Patients were treated with chlorambucil control (Arm 1), GAZYVA in combination with chlorambucil (Arm 2), or rituximab product in combination with chlorambucil (Arm 3). The safety and efficacy of GAZYVA was evaluated in a Stage 1 comparison of Arm 1 vs. Arm 2 in 356 patients and a Stage 2 comparison of Arm 2 vs. Arm 3 in 663 patients.

The majority of patients received 1,000 mg of GAZYVA on days 1, 8 and 15 of the first cycle, followed by treatment on the first day of 5 subsequent cycles (total of 6 cycles, 28 days each). The first dose of GAZYVA was divided between day 1 (100 mg) and day 2 (900 mg) [see Dosage and Administration (2.2)], which was implemented in 140 patients. Chlorambucil was given orally at 0.5 mg/kg on day 1 and day 15 of all treatment cycles (1 to 6).

In CLL11, the median age was 73 years, 62% were male, and 95% were White. Sixty-five percent had a CLcr < 70 mL/min and 76% had multiple coexisting medical conditions. Twenty-two percent of patients were Binet stage A, 42% were stage B, and 36% were stage C. The median estimated CLcr was 62 mL/min. Eighty-one percent of patients treated with GAZYVA in combination with chlorambucil received all 6 cycles compared to 89% of patients in the rituximab product treated arm and 67% in the chlorambucil alone arm.

In the Stage 1 analysis of CLL11, the median progression-free survival (PFS) in the GAZYVA in combination with chlorambucil arm was 27.2 months and 11.2 months in the chlorambucil alone arm (median observation time 22.8 months) as assessed by independent review and is consistent with investigator-assessed PFS. The median overall survival (OS) was not yet reached with a total of 46 deaths: 22 (9%) in the GAZYVA in combination with chlorambucil arm and 24 (20%) in the chlorambucil arm. The hazard ratio for OS was 0.41 (95% CI: 0.23-0.74).

In the Stage 2 analysis of CLL11, the median PFS was 26.7 months in the GAZYVA arm and 14.9 months in the rituximab product arm with a median observation time of 18.7 months (HR: 0.42, 95% CI: 0.33-0.54, p-value < 0.0001). These results were assessed by independent review and are consistent with investigator-assessed PFS. Minimal residual disease (MRD) was evaluated using allele-specific oligonucleotide polymerase chain reaction (ASO-PCR). The cutoff for a negative status was one CLL cell per 10^4 leukocytes in the sample (i.e., an MRD value of < 10^-4 was considered negative). Among patients who achieved complete response (CR) and complete response with incomplete marrow recovery (CRi; 94 patients in the GAZYVA arm and 34 patients in the rituximab product arm), 18 patients (19%) had negative MRD in the bone marrow in the GAZYVA arm compared to 2 patients (6%) in the rituximab product arm. Out of the patients who achieved CR and CRi, 39 patients (41%) in the GAZYVA arm, and 4 patients (12%) in the rituximab product arm were MRD negative in peripheral blood samples collected at least 3 months after the end of treatment.

Efficacy results are shown in Table 16 and Figures 1 and 2.

Table 16 Efficacy Results from CLL11
Endpoint | Stage 1 of CLL11 |  | Stage 2 of CLL11
Endpoint | GAZYVA + Chlorambucil [All Stage 1 GClb patients (n = 238) were included in the Stage 2 GClb population (n = 333).] | Chlorambucil | GAZYVA + Chlorambucil | Rituximab product + Chlorambucil
Endpoint | n = 238 | n = 118 | n = 333 | n = 330
Median Progression-Free Survival [As defined by independent review. Investigator-assessed PFS was consistent with data from independent review.] | 27.2 months | 11.2 months | 26.7 months | 14.9 months
Median Progression-Free Survival [As defined by independent review. Investigator-assessed PFS was consistent with data from independent review.] | (HR 0.19 [0.14; 0.27], p-value < 0.0001 stratified log-rank test) |  | (HR 0.42 [0.33; 0.54], p-value < 0.0001 stratified log-rank test)
Overall Response Rate [Defined as best overall response rate (ORR = CR + CRi + PR + nPR).] | 78.2% | 33.1% | 79.6% | 66.3%
Complete Response | 28.2% | 0 | 26.1% | 8.8%
Complete Response with Incomplete Marrow Recovery | 2.5% | 1.7% | 2.1% | 1.5%
Partial Response | 45.0% | 30.5% | 48.6% | 54.1%
Nodular Partial Response | 2.5% | 0.8% | 2.7% | 1.8%
Median Duration of Response | 22.4 months | 4.7 months | 19.6 months | 9.7 months
Overall Survival | HR 0.41 [0.23; 0.74] |  | Not Yet Mature

Figure 1
Kaplan-Meier Curve of Overall Survival in Patients with CLL in CLL11 (Stage 1)

Figure 2
Kaplan-Meier Curve of Progression-Free Survival in Patients with CLL in CLL11 (Stage 2)

14.2 Follicular Lymphoma

GADOLIN

The efficacy of GAZYVA was evaluated in GADOLIN (NCT01059630), an open-label, multicenter, randomized study that included 335 patients with follicular lymphoma (FL) who had no response to or have progressed during or within 6 months of rituximab product or a rituximab product-containing regimen. These patients were randomized to receive either bendamustine alone (n = 171) or GAZYVA in combination with bendamustine (n = 164) for 6 cycles, each of 28 days duration. Patients in the GAZYVA plus bendamustine arm who did not have disease progression [patients with a complete response (CR), partial response (PR) or stable disease (SD)] at the end of the 6 cycles continued receiving GAZYVA monotherapy for 2 years. Patients were stratified according to the type of refractoriness to rituximab product (refractory to rituximab product monotherapy versus rituximab product in combination with chemotherapy), the number of prior therapies (≤ 2 versus > 2), and geographic region.

GAZYVA was given by intravenous infusion as a flat dose of 1,000 mg on Days 1, 8 and 15 of Cycle 1, on Day 1 of Cycles 2–6, and then every 2 months until disease progression for up to 2 years. Bendamustine was given intravenously on Days 1 and 2 for all treatment cycles (1–6) at 90 mg/m^2/day when given in combination with GAZYVA or 120 mg/m^2/day when given alone.

The primary analysis included 321 FL patients, including 166 patients randomized to bendamustine alone and 155 patients randomized to GAZYVA in combination with bendamustine. In the primary analysis, patients had a median age of 63 years, 88% were White and 56% were male. Thirty-four percent had bulky disease (> 6 cm), 15% had at least one B-symptom at baseline and 95% had an ECOG performance status of 0–1 at baseline. The median time since initial diagnosis was 3 years and the median number of prior therapies was 2 (range 1 to 10). Forty-six percent of patients received 1 prior therapy and 33% of patients received 2 prior therapies. Twenty percent of patients were refractory to prior rituximab product monotherapy, 37% of patients were refractory to prior rituximab product plus chemotherapy induction treatment, and 41% of patients were refractory to rituximab product maintenance treatment received following rituximab product plus chemotherapy induction. Seventy-nine percent of patients were refractory to both rituximab product and an alkylating agent during any prior regimen (double refractory).

The major efficacy outcome measure was PFS as determined by an independent review committee (IRC). At the time of the primary analysis, median observation time was 21.1 months. The median PFS in the bendamustine arm was 13.8 months. Median PFS was not reached in the GAZYVA plus bendamustine arm (PFS HR = 0.48, 95% CI: 0.34-0.68; stratified log-rank test p-value < 0.0001). The investigator assessed PFS result was consistent with the IRC-assessed PFS. The median investigator-assessed PFS in the bendamustine arm was 13.7 months and the median in the GAZYVA containing arm was 29.2 months (PFS HR = 0.48, 95% CI: 0.35-0.67; stratified log-rank test p-value < 0.0001).

Efficacy results are summarized in Table 17. The Kaplan-Meier curve for IRC-PFS is shown in Figure 3.

Table 17 Primary Analysis Efficacy Results from GADOLIN [Based on FL population.] , [As defined by independent review.]
Endpoint | GADOLIN
Endpoint | GAZYVA + Bendamustine followed by GAZYVA monotherapy n = 155 | Bendamustine n = 166
Median Progression-Free Survival (months) | Not Reached | 13.8
Median Progression-Free Survival (months) | (HR = 0.48 [0.34; 0.68], p-value < 0.0001 by stratified log-rank test)
Best Overall Response [Best response of PR or CR within 12 months of study start.] | 78.7% | 74.7%
Complete Response | 15.5% | 18.7%
Partial Response | 63.2% | 56.0%
Median duration of response (months) | Not Reached | 11.6

Figure 3
Kaplan-Meier Curve of IRC-Assessed Progression-Free Survival in Patients with FL

The final analysis included a total of 335 patients with 171 randomized to bendamustine alone and 164 to GAZYVA in combination with bendamustine. With an overall median observation time of 52.2 months (range: 0-100.9 months), there were 66 deaths (40.2%) in the GAZYVA arm and 85 deaths (51.3%) in the bendamustine-alone arm (OS HR = 0.71, 95% CI: 0.51, 0.98). The Kaplan-Meier curve for OS is presented in Figure 4.

Figure 4
Kaplan-Meier Curve of Overall Survival in Patients with FL

GALLIUM

The efficacy of GAZYVA was evaluated in GALLIUM (NCT01332968), a multicenter, open-label, randomized study that included 1202 patients with previously untreated, stage II bulky, III or IV FL. Patients were randomized 1:1 to receive either GAZYVA (n = 601) or rituximab product (n = 601) in combination with chemotherapy (CHOP, CVP, or bendamustine) for 6–8 cycles. Patients were stratified by chemotherapy (selected by each site; all patients at that site received the chosen chemotherapy regimen), FLIPI (Follicular Lymphoma International Prognostic Index) risk group and geographic region. Patients with at least PR to combination therapy received monotherapy with GAZYVA (1,000 mg) or rituximab product every two months until disease progression or for a maximum of two years. The study excluded patients with follicular lymphoma grade 3b or transformed disease; patients having an ANC < 1500 / µL, platelets < 75,000 / µL, or CLcr < 40 mL/min; and patients with hepatic transaminases > 2.5 × upper limit of normal unless attributable to lymphoma.

GAZYVA was given by intravenous infusion as a flat dose of 1,000 mg on Days 1, 8 and 15 of Cycle 1 and Day 1 of subsequent treatment cycles.

GAZYVA and bendamustine were given in six 28-day cycles. Bendamustine was administered at 90 mg/m^2/day on Days 1 and 2 of each cycle, with prednisone 100 mg orally or equivalent on Day 1 of Cycle 1.

GAZYVA and CHOP were given in six 21-day cycles. Subsequently, two additional cycles of GAZYVA were given for a total of 8 GAZYVA cycles. CHOP consisted of cyclophosphamide 750 mg/m^2 intravenously, doxorubicin 50 mg/m^2, and vincristine 1.4 mg/m^2 (maximum dose, 2 mg) on Day 1 and prednisone 100 mg orally on Days 1-5.

GAZYVA and CVP were given in eight 21-day cycles. CVP consisted of cyclophosphamide 750 mg/m^2 intravenously and vincristine 1.4 mg/m^2 (maximum dose, 2 mg) on Day 1 and prednisone 100 mg orally on Days 1-5.

Patients had a median age of 59 years, 81% were White and 53% were female; 7% had Stage II, 35% had Stage III, and 56% had Stage IV disease, with 44% having bulky disease (≥ 7 cm) overall; 79% had a FLIPI score of > 2; and 97% had an ECOG performance status of 0–1. The chemotherapy was bendamustine in 57%, CHOP in 33%, and CVP in 10% of patients.

Efficacy was based on PFS per IRC, with a median observation time of 38 months. Upon interim analysis, the risk of progression or death was significantly reduced in the GAZYVA containing arm compared to the rituximab product containing arm (Table 18). Kaplan-Meier curves for PFS are shown in Figure 5. Overall response and complete remission rates were similar.

Table 18 Efficacy in Previously Untreated Follicular Lymphoma (GALLIUM)
Endpoint per IRC | GAZYVA + chemotherapy followed by GAZYVA monotherapy n = 601 | Rituximab product + chemotherapy followed by rituximab product monotherapy n = 601
Progression-Free Survival [Investigator-assessed PFS was consistent with data from independent review.] Number of events (%) | 108 (18%) | 141 (23%)
Progression-Free Survival [Investigator-assessed PFS was consistent with data from independent review.] Number of events (%) | HR = 0.72 [95% CI: 0.56, 0.93], p-value = 0.0118 [Stratified log-rank test.]
Overall Response Rate [After completion of combination therapy. Assessed by CT without positron emission tomography.] | 91% | 88%
Complete Remission Rate | 28% | 27%

Figure 5
Kaplan-Meier Curves of Progression Free Survival in Patients with Previously Untreated FL

14.3 Active Lupus Nephritis

Study Design and Population

The efficacy of GAZYVA was evaluated in REGENCY (NCT04221477), a Phase III, randomized, double-blind, placebo-controlled, parallel-group, multicenter study in 271 patients with ISN/RPS 2003 Class III or IV, with or without concomitant Class V lupus nephritis (LN), treated with standard therapy consisting of mycophenolate mofetil (MMF) and corticosteroids. Patients had active or active/chronic ISN/RPS 2003 Class III or IV, with or without concomitant Class V proliferative LN determined by kidney biopsy, current or past positive antinuclear antibody (ANA), urine protein-to-creatinine ratio (UPCR) ≥ 1 g/g, and had received at least one dose of pulse intravenous (IV) methylprednisolone (≥ 250 mg) or equivalent treatment for LN during the 6 months prior to screening or during screening.

Patients with estimated glomerular filtration rate (eGFR) <30 ml/min/1.73 m2 or in need of dialysis or transplantation, with sclerosis in > 50% of glomeruli on kidney biopsy, presence of rapidly progressive glomerulonephritis, evidence of active infection, receipt of anti-CD20 therapy < 9 months before or during screening, or receipt of cyclophosphamide, tacrolimus, ciclosporin, or voclosporin within 2 months of or during screening were excluded.

Patients were randomized 1:1 to receive GAZYVA 1,000 mg (N=135) or placebo (N=136) intravenously, in combination with MMF 2-2.5 g/day and a tapering course of corticosteroids and were evaluated over 76 weeks. Patients randomized to receive GAZYVA were further randomized in a 1:1 ratio to receive either GAZYVA 1,000 mg IV on Day 1, Weeks 2, 24, 26, 50, and 52 (Arm 1), or GAZYVA 1,000 mg IV on Day 1, Weeks 2, 24, 26, and 52 (Arm 2). The totality of the GAZYVA efficacy data combining both treatment arms is shown in Table 19.

All patients received oral prednisone 0.5 mg/kg/day (maximum 60 mg/day) and remained at this dose until Week 2. Beginning on Day 15, prednisone was tapered to achieve a target dose of 5 mg/day by Week 24. Prednisone was maintained at a low dose (5 mg/day) from Week 24 until Week 80.

The median age of patients was 31 years, 85% were female, 58% were Hispanic or Latino, 48% were White, 19% were American Indian or Alaska Native, 15% were Black or African American and 6% were Asian. The distribution by kidney biopsy class was 39% Class III, 61% Class IV and 31% had concomitant Class V. Mean (SD) eGFR at baseline 102.3 (±30.8) mL/min/1.73 m^2. Mean (SD) UPCR at baseline was 3.3 (±2.9) mg/mg with 42% of patients exhibiting UPCR ≥3 mg/mg at baseline.

Efficacy Results

The primary endpoint measure was proportion of patients who achieved complete renal response (CRR) at Week 76, defined as meeting all of the following criteria: UPCR < 0.5 g/g; eGFR ≥ 85% of baseline, as calculated using the 2009 Chronic Kidney Disease Epidemiology Collaboration (CKD-EPI) equation; with no occurrence of the following intercurrent events: rescue therapy, treatment failure, death or early study withdrawal.

Key secondary endpoint measures included: proportion of patients who achieved CRR with successful prednisone taper at Week 76 (defined as achievement of CRR at Week 76 without receiving prednisone > 7.5 mg/day or equivalent from Week 64 through Week 76), proportion of patients who achieved a proteinuric response at Week 76 (defined as achievement of UPCR < 0.8g/g and no occurrence of the following intercurrent events: rescue therapy, treatment failure, death or early study withdrawal) and proportion of patients who experience "renal-related events or deaths" through Week 76 (defined as occurrence of death, treatment failure, ≥ 50% increase in UPCR to a value ≥ 3 g/g and/or ≥ 30% decrease in eGFR to < 60 ml/min/1.73 m^2).

The proportion of patients achieving CRR at Week 76 was significantly greater in patients treated with GAZYVA in combination with standard therapy compared to patients who received placebo plus standard therapy. There were also a higher proportion of patients who achieved CRR with successful prednisone taper at Week 76 and proteinuric response at Week 76 in the GAZYVA plus standard therapy arm compared to the placebo plus standard therapy arm (see Table 19).

In the REGENCY study, patients who received GAZYVA were less likely to experience the outcome of "renal-related event or death" compared with placebo. Fewer patients in the GAZYVA arm experienced worsening kidney function or doubling of serum creatinine (see Table 20).

Table 19 Summary of Efficacy Results in Adult Patients with Active Lupus Nephritis (REGENCY Study)
 | GAZYVA + standard therapy (N=135) | Placebo + standard therapy (N=136)
Primary Endpoint
Complete renal response (CRR) at Week 76 (%) | 46.4 (38.0, 54.9) | 33.1 (25.2, 41)
Treatment difference (95% CI) [Primary and key secondary endpoints were analyzed using the Cochran-Mantel-Haenszel (CMH) test, adjusted for stratification factors race and region. Multiple Imputation handled missing data. For the primary endpoint CRR and the key secondary endpoint CRR with successful prednisone taper, missing data (not due to an Intercurrent Event (ICE)) occurred in four patients in the GAZYVA arm and one in the placebo arm. For the key secondary endpoint proteinuric response, four GAZYVA patients and two placebo patients had non-ICE-related missing data.] | 13.4 (2.0, 24.8)
p-value | 0.0232
Components of CRR:
UPCR < 0.5 g/g | 64 (47.4%) | 49 (36.0%)
eGFR ≥ 85% at baseline | 113 (83.7%) | 103 (75.7%)
No occurrence of intercurrent events | 120 (88.9%) | 102 (75%)
Key Secondary Endpoints
CRR with successful prednisone taper at Week 76 (%) | 42.7 (34.3, 51.1) | 30.9 (23.1, 38.7)
Treatment difference (95% CI) | 11.9 (0.6, 23.2)
p-value | 0.0421
Proteinuric response at Week 76 (%) | 55.5 (47.1, 64) | 41.9 (33.6, 50.2)
Treatment difference (95% CI) | 13.7 (2.0, 25.4),
p-value | 0.0227

Table 20 Renal-Related Event or Death in Adult Patients with Active Lupus Nephritis (REGENCY Study) by Week 76
 | Week 0-76 |  | Hazard Ratio (HR) vs. Placebo (95% CI) Week 76
 | GAZYVA + standard therapy N=135 (%) | Placebo + standard therapy N=136 (%) | Hazard Ratio (HR) vs. Placebo (95% CI) Week 76
Renal-Related Event or Death
Number (%) of patients with event | 24 (17.8%) | 46 (33.8%)
Time to event |  |  | 0.5 (0.3, 0.8)
Components of Renal-Related Event or Death Endpoint
Percentage of patients with:
Death | 3 (2.2%) | 1 (0.7%)
Treatment failure [Treatment failure was prospectively defined as any of the following: 1) new ESRD or need for chronic dialysis or renal transplantation, 2) clinically significant, sustained worsening in UPCR and/or eGFR from Week 24 onward that leads the investigator to conclude the patient failed the randomized treatment period, or 3) receipt of rescue therapy, except corticosteroid-only rescue] | 6 (4.4%) | 25 (18.4%)
End-stage renal disease (ESRD)^1 | 0 | 2 (1.5%)
Clinically significant, sustained worsening in UPCR and/or eGFR from Week 24^2 | 5 (3.7%) | 22(16.2%)
Rescue Therapy except corticosteroid-only rescue^3 | 5 (3.7%) | 22 (16.2%)
Worsening proteinuria [Worsening proteinuria was prospectively defined as a confirmed ≥ 50% increase in UPCR to a value ≥ 3 g/g] | 17 (12.6%) | 18 (13.2%)
Worsening eGFR [Worsening eGFR was prospectively defined as confirmed ≥ 30% decrease in eGFR to a value < 60mL/min/1.73m^2] | 7 (5.2%) | 20 (14.7%)
Additional Renal-Related Events
Percentage of patients with event
Doubling of serum creatinine from baseline through Week 76 | 4 (3.0%) | 8 (5.9%)

Subgroup Analyses

In pre-specified subgroup efficacy analyses, the primary endpoint in patients was examined based on 24-hour UPCR at baseline (< 3 g/g or ≥ 3 g/g), lupus nephritis class at baseline (Class III or IV), and concomitant Class V at baseline. The results are displayed in Figure 6 below.

Figure 6
Forest Plot of CRR at Week 76 on Baseline Disease Characteristics, Efficacy-Evaluable Patients

16 HOW SUPPLIED/STORAGE AND HANDLING

GAZYVA (obinutuzumab) injection is a clear, colorless to slightly brown, preservative-free solution for intravenous use supplied as 1,000 mg/40 mL (25 mg/mL) in single-dose vials (NDC 50242-070-01).

STORAGE AND HANDLING

Store at 2°C to 8°C (36°F to 46°F). Do not use beyond expiration date stamped on carton. Protect from light. DO NOT FREEZE. DO NOT SHAKE.

17 PATIENT COUNSELING INFORMATION

Infusion-related Reactions

Advise patients to seek immediate medical attention if signs and symptoms of infusion-related reactions occur [see Warnings and Precautions (5.3) and Adverse Reactions (6.1 and 6.2)].

Tumor Lysis Syndrome

Advise patients to seek immediate medical attention if symptoms of tumor lysis syndrome occur [see Warnings and Precautions (5.5) and Adverse Reactions (6.1)].

Infections

Advise patients to seek immediate medical attention if signs of an infection occur [see Warnings and Precautions (5.6) and Adverse Reactions (6.1 and 6.2)].

Hepatitis B Virus Reactivation

Advise patients to seek immediate medical attention if symptoms of hepatitis occur [see Warnings and Precautions (5.1)]. Advise patients of the need for hepatitis B virus screening and monitoring during treatment with GAZYVA.

Progressive Multifocal Leukoencephalopathy

Advise patients to seek immediate medical attention if new or changes in neurological symptoms occur [see Warnings and Precautions (5.2)].

Neutropenia, Thrombocytopenia and Disseminated Intravascular Coagulation

Advise patients to seek immediate medical attention if signs and symptoms of bleeding or thrombosis occur. Advise patients of the need for periodic monitoring of blood counts [see Warnings and Precautions (5.7, 5.8 and 5.9) and Adverse Reactions (6.1 and 6.2)].

Immunization

Advise patients to avoid vaccinations with live viral vaccines [see Warnings and Precautions (5.10)].

Embryo-Fetal Toxicity

Advise pregnant women of potential fetal B-cell depletion. Advise females of reproductive potential to inform their healthcare provider of a known or suspected pregnancy [see Warnings and Precautions (5.11), Use in Specific Populations (8.1)].

Contraception

Advise females of reproductive potential to use effective contraception during treatment with GAZYVA and for 6 months after the last dose [see Use in Specific Populations (8.3)].

Lactation

Advise women not to breastfeed during treatment with GAZYVA and for 6 months after the last dose [see Use in Specific Populations (8.2)].

GAZYVA® (obinutuzumab)

Manufactured by:
Genentech, Inc.
A Member of the Roche Group
1 DNA Way
South San Francisco, CA 94080-4990
U.S. License No. 1048

GAZYVA is a registered trademark of Genentech, Inc.
© 2025 Genentech, Inc.

PRINCIPAL DISPLAY PANEL - 40 mL Vial Carton

NDC 50242-070-01

Gazyva®
(obinutuzumab)
Injection

1000 mg/40 mL
(25 mg/mL)

For Intravenous Infusion After Dilution.
Single-Dose Vial. Discard Unused Portion.
No preservative.

1 vial

Rx only

Genentech

10240530